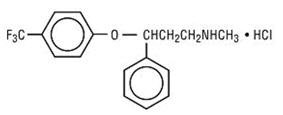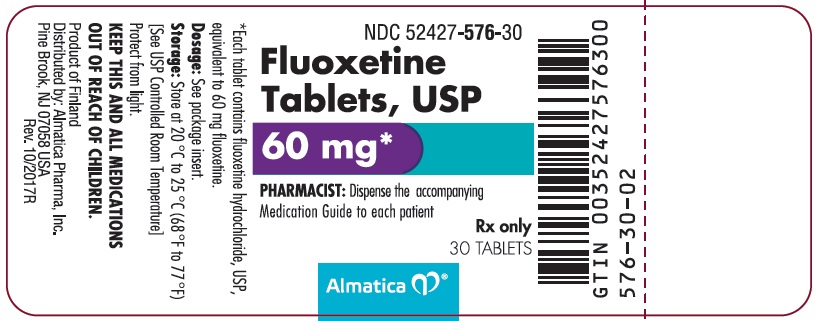 DRUG LABEL: Fluoxetine HCl
NDC: 52427-576 | Form: TABLET, FILM COATED
Manufacturer: Almatica Pharma Inc.
Category: prescription | Type: HUMAN PRESCRIPTION DRUG LABEL
Date: 20240501

ACTIVE INGREDIENTS: FLUOXETINE HYDROCHLORIDE 60 mg/1 1
INACTIVE INGREDIENTS: MANNITOL; MICROCRYSTALLINE CELLULOSE; STARCH, CORN; POVIDONE, UNSPECIFIED; HYPROMELLOSE, UNSPECIFIED; MAGNESIUM STEARATE; TITANIUM DIOXIDE; SUCROSE; GLYCERIN; POLYSORBATE 80

HIGHLIGHTS OF PRESCRIBING INFORMATION

These highlights do not include all the information needed to use FLUOXETINE TABLETS safely and effectively. See full prescribing information for FLUOXETINE TABLETS.
FLUOXETINE tablets, for oral use
Initial U.S. Approval: 1987

RECENT MAJOR CHANGES

Warnings and Precautions (5.2, 5.7) | 8/2023

WARNING: SUICIDAL THOUGHTS AND BEHAVIORS

See full prescribing information for complete boxed warning.

- Increased risk of suicidal thinking and behavior in children, adolescents, and young adults taking antidepressants (5.1).
- Monitor for worsening and emergence of suicidal thoughts and behaviors (5.1).

1 INDICATIONS AND USAGE

Fluoxetine tablets are a selective serotonin reuptake inhibitor (SSRI) indicated for the treatment of:

- Major Depressive Disorder (MDD) (1)
  - Adults: Efficacy was established in one 5-week trial, three 6-week trials, and one maintenance study (14.1)
  - Pediatrics: Efficacy was established in two 8- to 9-week trials of patients 8 to 18 years of age (14.1)
- Obsessive Compulsive Disorder (OCD) (1)
  - Adults: Efficacy was established in two 13-week trials (14.2)
  - Pediatrics: Efficacy was established in one 13-week trial in patients 7 to 17 years of age (14.2)
- Bulimia Nervosa (1)
  - Adults: Efficacy was established in two 8-week trials and one 16-week trial (14.3)
- Panic Disorder, with or without agoraphobia (1)
  - Adults: Efficacy was established in two 12-week trials (14.4)

2 DOSAGE AND ADMINISTRATION

- Use another fluoxetine product for initial doses of 10 to 20 mg/day or for doses other than 30 mg or 60 mg:

Indication | Adult | Pediatric
MDD (2.1) | 20 mg/day in morning (initial dose); 20 mg/day (target dose); 80 mg/day (maximum dose studied) | 10 to 20 mg/day (initial dose)*; *This product has not been studied in doses greater than 20 mg/day in pediatric MDD.
OCD (2.2) | 20 mg/day in morning (initial dose); 20 to 60 mg/day (target dose) | 10 mg/day (initial dose); 10 to 60 mg/day (target dose)
Bulimia Nervosa (2.3) | 60 mg/day in morning | -
Panic Disorder (2.4) | 10 mg/day (initial dose); 20 mg/day (target dose); 60 mg/day (maximum dose studied) | -

- No additional benefits seen at higher doses above 20 mg/day in MDD (2.1, 14.1)
- Use a lower or less frequent dosage in patients with hepatic impairment, the elderly, and for patients with concurrent disease or on multiple concomitant medications (2.5, 8.6)

3 DOSAGE FORMS AND STRENGTHS

- Tablets: 60 mg, functionally scored (3)

4 CONTRAINDICATIONS

- Monoamine Oxidase Inhibitors (MAOIs): Do not use MAOIs intended to treat psychiatric disorders with fluoxetine or within 5 weeks of stopping treatment with fluoxetine. Do not use fluoxetine within 14 days of stopping an MAOI intended to treat psychiatric disorders. In addition, do not start fluoxetine in a patient who is being treated with linezolid or intravenous methylene blue (4.1, 7.1)
- Pimozide: (4.2, 5.11, 7.6, 7.7)
- Thioridazine: Do not use concomitantly with or within 5 weeks of discontinuing fluoxetine (4.2, 5.11, 7.6, 7.7)
- Known hypersensitivity to fluoxetine products (4.2, 5.3)

5 WARNINGS AND PRECAUTIONS

- Suicidal Thoughts and Behaviors in Children, Adolescents, and Young Adults: Monitor for clinical worsening and suicidal thinking and behavior (5.1)
- Serotonin Syndrome: Serotonin syndrome has been reported with SSRIs and serotonin-norepinephrine reuptake inhibitors (SNRIs), including fluoxetine, both when taken alone, but especially when co-administered with other serotonergic agents. If such symptoms occur, discontinue fluoxetine and serotonergic agents and initiate supportive treatment. If concomitant use of fluoxetine with other serotonergic drugs is clinically warranted, patients should be made aware of a potential increased risk for serotonin syndrome, particularly during treatment initiation and dose increases (5.2)
- Activation of Mania/Hypomania: Screen for Bipolar Disorder and monitor for mania/hypomania (5.4)
- Seizures: Use cautiously in patients with a history of seizures or with conditions that potentially lower the seizure threshold (5.5)
- Altered Appetite and Weight: Significant weight loss has occurred (5.6)
- Increased Risk of Bleeding: May increase the risk of bleeding. Use with NSAIDs, aspirin, warfarin, or drugs that affect coagulation may potentiate the risk of gastrointestinal or other bleeding (5.7, 7.4)
- Angle-closure Glaucoma: Angle-closure glaucoma has occurred in patients with untreated anatomically narrow angles treated with antidepressants (5.8)
- Hyponatremia: Has been reported with fluoxetine in association with syndrome of inappropriate antidiuretic hormone (SIADH). Consider discontinuing if symptomatic hyponatremia occurs (5.9)
- QT Prolongation: QT prolongation and ventricular arrhythmia including Torsades de Pointes have been reported with fluoxetine use. Use with caution in conditions that predispose to arrhythmias or increase fluoxetine exposure. Use cautiously in patients with risk factors for QT prolongation (4.2, 5.11, 7.6, 7.7, 10)
- Long Half-life: Changes in dose will not be fully reflected in plasma for several weeks (5.14)
- Sexual Dysfunction: Fluoxetine may cause symptoms of sexual dysfunction (5.16)

6 ADVERSE REACTIONS

Most common adverse reactions (≥ 5% and at least twice that for placebo): abnormal dreams, abnormal ejaculation, anorexia, anxiety, asthenia, diarrhea, dry mouth, dyspepsia, flu syndrome, impotence, insomnia, libido decreased, nausea, nervousness, pharyngitis, rash, sinusitis, somnolence, sweating, tremor, vasodilatation, and yawn (6.1)

To report SUSPECTED ADVERSE REACTIONS, contact Almatica Pharma, Inc. at 1-877-447-7979 or FDA at 1-800-FDA-1088 or www.fda.gov/medwatch.

7 DRUG INTERACTIONS

- Drugs Metabolized by CYP2D6: Fluoxetine is a potent inhibitor of CYP2D6 enzyme pathway (7.6)
- Tricyclic Antidepressants (TCAs): Monitor TCA levels during co-administration with fluoxetine or when fluoxetine has been recently discontinued (5.2, 7.6)
- Benzodiazepines: Diazepam—increased t1/2, alprazolam—further psychomotor performance decrement due to increased levels (7.6)
- Antipsychotics: Potential for elevation of haloperidol and clozapine levels (7.6)
- Anticonvulsants: Potential for elevated phenytoin and carbamazepine levels and clinical anticonvulsant toxicity (7.6)
- Serotonergic Drugs: (2.6, 2.7, 4.1, 5.2)
- Drugs that Prolong the QT Interval: Do not use fluoxetine with thioridazine or pimozide. Use with caution in combination with other drugs that prolong the QT interval (4.2, 5.11, 7.6, 7.7)

8 USE IN SPECIFIC POPULATIONS

- Pregnancy: SSRI use, particularly later in pregnancy, may increase risk for persistent pulmonary hypertension and symptoms of poor adaptation (respiratory distress, temperature instability, feeding difficulty, hypotonia, tremor, irritability) in the neonate (8.1)
- Pediatric Use: Safety and effectiveness of fluoxetine in patients < 8 years of age with MDD and < 7 years of age with OCD have not been established (8.4)

FULL PRESCRIBING INFORMATION

WARNING: SUICIDAL THOUGHTS AND BEHAVIORS

- Antidepressants increased the risk of suicidal thoughts and behavior in children, adolescents, and young adults in short-term studies. These studies did not show an increase in the risk of suicidal thoughts and behavior with antidepressant use in patients over age 24; there was a reduction in risk with antidepressant use in patients aged 65 and older [see Warnings and Precautions (5.1)].
- In patients of all ages who are started on antidepressant therapy, monitor closely for worsening and for emergence of suicidal thoughts and behavior. Advise families and caregivers of the need for close observation and communication with the prescriber [see Warnings and Precautions (5.1)].
- Fluoxetine is not approved for use in children less than 7 years of age [see Warnings and Precautions (5.1) and Use in Specific Populations (8.4)] .

1 INDICATIONS AND USAGE

Fluoxetine tablets are indicated for the treatment of:

- Major Depressive Disorder (MDD). The efficacy of fluoxetine in MDD was established in one 5-week trial, three 6-week trials, and one maintenance study in adults. The efficacy of fluoxetine was also established in two 8- to 9-week trials in pediatric patients 8 to 18 years of age [see Clinical Studies (14.1)].
- Obsessions and compulsions in patients with Obsessive Compulsive Disorder (OCD). The efficacy of fluoxetine in OCD was demonstrated in two 13-week trials in adults and one 13-week trial in pediatric patients 7 to 17 years of age [see Clinical Studies (14.2)].
- Binge-eating and vomiting behaviors in patients with moderate to severe Bulimia Nervosa. The efficacy of fluoxetine in Bulimia Nervosa was demonstrated in two 8-week trials and one 16-week trial in adults [see Clinical Studies (14.3)].
- Panic Disorder, with or without agoraphobia. The efficacy of fluoxetine in Panic Disorder was demonstrated in two 12-week trials in adults [see Clinical Studies (14.4)].

2 DOSAGE AND ADMINISTRATION

This product is only available in a 60 mg dosage form. A 30 mg dose may be achieved with one-half of the scored tablet. Use of this product requires initial titration with another fluoxetine product according to the dosing guidelines indicated below.

2.1 Major Depressive Disorder

Initial Treatment

Adult—Initiate fluoxetine 20 mg/day orally in the morning. Consider a dose increase after several weeks if insufficient clinical improvement is observed. Administer doses above 20 mg/day once daily in the morning or twice daily (i.e., morning and noon). The maximum fluoxetine dose should not exceed 80 mg/day.

In controlled trials used to support the efficacy of fluoxetine, patients were administered morning doses ranging from 20 to 80 mg/day. Studies comparing fluoxetine 20, 40, and 60 mg/day to placebo indicate that 20 mg/day is sufficient to obtain a satisfactory response in MDD in most cases [see Clinical Studies (14.1)].

Pediatric (children and adolescents)—Treatment should be initiated with a dose of 10 or 20 mg/day. After 1 week at 10 mg/day, the dose should be increased to 20 mg/day. However, due to higher plasma levels in lower weight children, the starting and target dose in this group may be 10 mg/day. A dose increase to 20 mg/day may be considered after several weeks if insufficient clinical improvement is observed. In the short-term (8- to 9-week) controlled clinical trials of fluoxetine supporting its effectiveness in the treatment of MDD, patients were administered fluoxetine doses of 10 to 20 mg/day [see Clinical Studies (14.1)]. Doses greater than 20 mg/day have not been studied in pediatric patients with MDD. This product is only available in a 60 mg dosage form. Administration of doses with demonstrated efficacy of fluoxetine 10 to 20 mg/day in pediatric MDD requires the use of another formulation.

All patients—As with other drugs effective in the treatment of MDD, the full effect may be delayed until 4 weeks of treatment or longer.

Periodically reassess to determine the need for maintenance treatment.

Switching Patients to a Tricyclic Antidepressant (TCA)—Dosage of a TCA may need to be reduced, and plasma TCA concentrations may need to be monitored temporarily when fluoxetine is co-administered or has been recently discontinued [see Warnings and Precautions (5.2) and Drug Interactions (7.6)].

2.2 Obsessive Compulsive Disorder

Initial Treatment

Adults—Initiate fluoxetine 20 mg/day, orally in the morning. Consider a dose increase after several weeks if insufficient clinical improvement is observed. The full therapeutic effect may be delayed until 5 weeks of treatment or longer.

Doses above 20 mg/day may be administered on a once daily (i.e., morning) or twice daily schedule (i.e., morning and noon). A dose range of 20 to 60 mg/day is recommended; however, doses of up to 80 mg/day have been well tolerated in open studies of OCD. The maximum fluoxetine dose should not exceed 80 mg/day.

In the controlled clinical trials of fluoxetine supporting its effectiveness in the treatment of OCD, patients were administered fixed daily doses of 20, 40, or 60 mg of fluoxetine or placebo [see Clinical Studies (14.2)]. In one of these studies, no dose-response relationship for effectiveness was demonstrated.

Pediatric (children and adolescents)—In adolescents and higher weight children, treatment should be initiated with a dose of 10 mg/day. After 2 weeks, the dose should be increased to 20 mg/day. Additional dose increases may be considered after several more weeks if insufficient clinical improvement is observed. A dose range of 20 to 60 mg/day is recommended.

In lower weight children, treatment should be initiated with a dose of 10 mg/day. Additional dose increases may be considered after several more weeks if insufficient clinical improvement is observed. A dose range of 20 to 30 mg/day is recommended. Experience with daily doses greater than 20 mg is very minimal, and there is no experience with doses greater than 60 mg.

In the controlled clinical trial of fluoxetine supporting its effectiveness in the treatment of OCD, patients were administered fluoxetine doses in the range of 10 to 60 mg/day [see Clinical Studies (14.2)].

Periodically reassess to determine the need for treatment.

2.3 Bulimia Nervosa

Initial Treatment—Administer fluoxetine 60 mg/day in the morning. For some patients it may be advisable to titrate up to this target dose over several days. Fluoxetine doses above 60 mg/day have not been systematically studied in patients with Bulimia Nervosa. In the controlled clinical trials of fluoxetine supporting its effectiveness in the treatment of Bulimia Nervosa, patients were administered fixed daily fluoxetine doses of 20 or 60 mg, or placebo [see Clinical Studies (14.3)]. Only the 60 mg dose was statistically significantly superior to placebo in reducing the frequency of binge-eating and vomiting.

Periodically reassess to determine the need for maintenance treatment.

2.4 Panic Disorder

Initial Treatment —Treatment should be initiated with a dose of 10 mg/day. After 1 week, the dose should be increased to 20 mg/day. A dose increase may be considered after several weeks if no clinical improvement is observed. Fluoxetine doses above 60 mg/day have not been systematically evaluated in patients with Panic Disorder. In the controlled clinical trials of fluoxetine supporting its effectiveness in the treatment of Panic Disorder, patients were administered fluoxetine doses in the range of 10 to 60 mg/day [see Clinical Studies (14.4)]. The most frequently administered dose in the 2 flexible-dose clinical trials was 20 mg/day.

Periodically reassess to determine the need for continued treatment.

2.5 Dosing in Specific Populations

Geriatrics—A lower or less frequent dosage should be considered for the elderly [see Use in Specific Populations (8.5)].

Hepatic Impairment—As with many other medications, a lower or less frequent dosage should be used in patients with hepatic impairment [see Clinical Pharmacology (12.3) and Use in Specific Populations (8.6)].

2.6 Switching a Patient To or From a Monoamine Oxidase Inhibitor (MAOI) Intended to Treat Psychiatric Disorders

At least 14 days should elapse between discontinuation of an MAOI intended to treat psychiatric disorders and initiation of therapy with fluoxetine. Conversely, at least 5 weeks should be allowed after stopping fluoxetine before starting an MAOI intended to treat psychiatric disorders [see Contraindications (4.1)].

2.7 Use of Fluoxetine with Other MAOIs Such as Linezolid or Methylene Blue

Do not start fluoxetine in a patient who is being treated with linezolid or intravenous methylene blue because there is an increased risk of serotonin syndrome. In a patient who requires more urgent treatment of a psychiatric condition, other interventions, including hospitalization, should be considered [see Contraindications (4.1)].

In some cases, a patient already receiving fluoxetine therapy may require urgent treatment with linezolid or intravenous methylene blue. If acceptable alternatives to linezolid or intravenous methylene blue treatment are not available and the potential benefits of linezolid or intravenous methylene blue treatment are judged to outweigh the risks of serotonin syndrome in a particular patient, fluoxetine should be stopped promptly, and linezolid or intravenous methylene blue can be administered. The patient should be monitored for symptoms of serotonin syndrome for 5 weeks or until 24 hours after the last dose of linezolid or intravenous methylene blue, whichever comes first. Therapy with fluoxetine may be resumed 24 hours after the last dose of linezolid or intravenous methylene blue [see Warnings and Precautions (5.2)].

The risk of administering methylene blue by nonintravenous routes (such as oral tablets or by local injection) or in intravenous doses much lower than 1 mg/kg with fluoxetine is unclear. The clinician should, nevertheless, be aware of the possibility of emergent symptoms of serotonin syndrome with such use [see Warnings and Precautions (5.2)].

3 DOSAGE FORMS AND STRENGTHS

Tablets: 60 mg (fluoxetine base equivalent), film coated, functionally scored, capsule-shaped, white tablets debossed with “FL 60” on one side (“FL” above the score and “60” below the score).

4 CONTRAINDICATIONS

4.1 Monoamine Oxidase Inhibitors (MAOIs)

The use of MAOIs intended to treat psychiatric disorders with fluoxetine or within 5 weeks of stopping treatment with fluoxetine is contraindicated because of an increased risk of serotonin syndrome. The use of fluoxetine within 14 days of stopping an MAOI intended to treat psychiatric disorders is also contraindicated [see Dosage and Administration (2.6) and Warnings and Precautions (5.2)].

Starting fluoxetine in a patient who is being treated with MAOIs such as linezolid or intravenous methylene blue is also contraindicated because of an increased risk of serotonin syndrome [see Dosage and Administration (2.7) and Warnings and Precautions (5.2)].

4.2 Other Contraindications

The use of fluoxetine is contraindicated with the following:

- Pimozide [see Warnings and Precautions (5.11) and Drug Interactions (7.6, 7.7)]
- Thioridazine [see Warnings and Precautions (5.11) and Drug Interactions (7.6, 7.7)]

Pimozide and thioridazine prolong the QT interval. Fluoxetine can increase the levels of pimozide and thioridazine through inhibition of CYP2D6. Fluoxetine can also prolong the QT interval.

- Known hypersensitivity to fluoxetine: Do not use this product in patients with known hypersensitivity to fluoxetine due to risk of anaphylactoid reactions, including bronchospasm, angioedema, laryngospasm, and urticaria [see Warnings and Precautions (5.3)].

5 WARNINGS AND PRECAUTIONS

5.1 Suicidal Thoughts and Behaviors in Children, Adolescents, and Young Adults

Patients with MDD, both adult and pediatric, may experience worsening of their depression and/or the emergence of suicidal ideation and behavior (suicidality) or unusual changes in behavior, whether or not they are taking antidepressant medications, and this risk may persist until significant remission occurs. Suicide is a known risk of depression and certain other psychiatric disorders, and these disorders themselves are the strongest predictors of suicide. There has been a long-standing concern, however, that antidepressants may have a role in inducing worsening of depression and the emergence of suicidality in certain patients during the early phases of treatment. Pooled analyses of short-term placebo-controlled trials of antidepressant drugs (SSRIs and others) showed that these drugs increase the risk of suicidal thinking and behavior (suicidality) in children, adolescents, and young adults (ages 18 to 24) with MDD and other psychiatric disorders. Short-term studies did not show an increase in the risk of suicidality with antidepressants compared to placebo in adults beyond age 24; there was a reduction with antidepressants compared to placebo in adults aged 65 and older.

The pooled analyses of placebo-controlled trials in children and adolescents with MDD, OCD, or other psychiatric disorders included a total of 24 short-term trials of 9 antidepressant drugs in over 4400 patients. The pooled analyses of placebo-controlled trials in adults with MDD or other psychiatric disorders included a total of 295 short-term trials (median duration of 2 months) of 11 antidepressant drugs in over 77,000 patients. There was considerable variation in risk of suicidality among drugs, but a tendency toward an increase in the younger patients for almost all drugs studied. There were differences in absolute risk of suicidality across the different indications, with the highest incidence in MDD. The risk differences (drug versus placebo), however, were relatively stable within age strata and across indications. These risk differences (drug-placebo difference in the number of cases of suicidality per 1000 patients treated) are provided in Table 1.

Table 1. Risk Differences in the Number of Suicidality Cases by Age Group in the Pooled Placebo-controlled Trials of Antidepressants in Pediatric and Adult Patients
Age Range (years) | Drug-Placebo Difference in Number of Cases of Suicidality per 1000 Patients Treated
 | Increases Compared to Placebo
< 18 | 14 additional cases
18-24 | 5 additional cases
 | Decreases Compared to Placebo
25-64 | 1 fewer case
≥ 65 | 6 fewer cases

No suicides occurred in any of the pediatric trials. There were suicides in the adult trials, but the number was not sufficient to reach any conclusion about drug effect on suicide.

It is unknown whether the suicidality risk extends to longer-term use, i.e., beyond several months. However, there is substantial evidence from placebo-controlled maintenance trials in adults with depression that the use of antidepressants can delay the recurrence of depression.

All patients being treated with antidepressants for any indication should be monitored appropriately and observed closely for clinical worsening, suicidality, and unusual changes in behavior, especially during the initial few months of a course of drug therapy, or at times of dose changes, either increases or decreases.

The following symptoms, anxiety, agitation, panic attacks, insomnia, irritability, hostility, aggressiveness, impulsivity, akathisia (psychomotor restlessness), hypomania, and mania, have been reported in adult and pediatric patients being treated with antidepressants for MDD as well as for other indications, both psychiatric and nonpsychiatric. Although a causal link between the emergence of such symptoms and either the worsening of depression and/or the emergence of suicidal impulses has not been established, there is concern that such symptoms may represent precursors to emerging suicidality.

Consideration should be given to changing the therapeutic regimen, including possibly discontinuing the medication, in patients whose depression is persistently worse, or who are experiencing emergent suicidality or symptoms that might be precursors to worsening depression or suicidality, especially if these symptoms are severe, abrupt in onset, or were not part of the patient’s presenting symptoms.

If the decision has been made to discontinue treatment, medication should be tapered, as rapidly as is feasible, but with recognition that abrupt discontinuation can be associated with certain symptoms [see Warnings and Precautions (5.15)].

Families and caregivers of patients being treated with antidepressants for MDD or other indications, both psychiatric and nonpsychiatric, should be alerted about the need to monitor patients for the emergence of agitation, irritability, unusual changes in behavior, and the other symptoms described above, as well as the emergence of suicidality, and to report such symptoms immediately to health care providers. Such monitoring should include daily observation by families and caregivers. Prescriptions for fluoxetine should be written for the smallest quantity of tablets consistent with good patient management, in order to reduce the risk of overdose.

It should be noted that fluoxetine is approved in the pediatric population only for MDD and OCD.

5.2 Serotonin Syndrome

Selective serotonin reuptake inhibitors (SSRIs), including fluoxetine, can precipitate serotonin syndrome, a potentially life-threatening condition. The risk is increased with concomitant use of other serotonergic drugs (including triptans, tricyclic antidepressants, fentanyl, lithium, tramadol, meperidine, methadone, tryptophan, buspirone, amphetamines, and St. John’s Wort) and with drugs that impair metabolism of serotonin, i.e., MAOIs [see Contraindications (4), Drug Interactions (7.1, 7.3)]. Serotonin syndrome can also occur when these drugs are used alone.

Serotonin syndrome signs and symptoms may include mental status changes (e.g., agitation, hallucinations, delirium, and coma), autonomic instability (e.g., tachycardia, labile blood pressure, dizziness, diaphoresis, flushing, hyperthermia), neuromuscular symptoms (e.g., tremor, rigidity, myoclonus, hyperreflexia, incoordination), seizures, and gastrointestinal symptoms (e.g., nausea, vomiting, diarrhea).

The concomitant use of fluoxetine with MAOIs is contraindicated. In addition, do not initiate fluoxetine in a patient being treated with MAOIs such as linezolid or intravenous methylene blue. No reports involved the administration of methylene blue by other routes (such as oral tablets or local tissue injection). If it is necessary to initiate treatment with an MAOI such as linezolid or intravenous methylene blue in a patient taking fluoxetine, discontinue fluoxetine before initiating treatment with the MAOI [see Contraindications (4), Drug Interactions (7.1)].

Monitor all patients taking fluoxetine for the emergence of serotonin syndrome. Discontinue treatment with fluoxetine and any concomitant serotonergic agents immediately if the above symptoms occur, and initiate supportive symptomatic treatment. If concomitant use of fluoxetine with other serotonergic drugs is clinically warranted, inform patients of the increased risk for serotonin syndrome and monitor for symptoms.

5.3 Allergic Reactions and Rash

In US fluoxetine clinical trials, 7% of 10,782 patients developed various types of rashes and/or urticaria. Among the cases of rash and/or urticaria reported in premarketing clinical trials, almost a third were withdrawn from treatment because of the rash and/or systemic signs or symptoms associated with the rash. Clinical findings reported in association with rash include fever, leukocytosis, arthralgias, edema, carpal tunnel syndrome, respiratory distress, lymphadenopathy, proteinuria, and mild transaminase elevation. Most patients improved promptly with discontinuation of fluoxetine and/or adjunctive treatment with antihistamines or steroids, and all patients experiencing these reactions were reported to recover completely.

In premarketing clinical trials, 2 patients are known to have developed a serious cutaneous systemic illness. In neither patient was there an unequivocal diagnosis, but one was considered to have a leukocytoclastic vasculitis, and the other, a severe desquamating syndrome that was considered variously to be a vasculitis or erythema multiforme. Other patients have had systemic syndromes suggestive of serum sickness.

Since the introduction of fluoxetine, systemic reactions, possibly related to vasculitis and including lupus-like syndrome, have developed in patients with rash. Although these reactions are rare, they may be serious, involving the lung, kidney, or liver. Death has been reported to occur in association with these systemic reactions.

Anaphylactoid reactions, including bronchospasm, angioedema, laryngospasm, and urticaria alone and in combination, have been reported.

Pulmonary reactions, including inflammatory processes of varying histopathology and/or fibrosis, have been reported rarely. These reactions have occurred with dyspnea as the only preceding symptom.

Whether these systemic reactions and rash have a common underlying cause or are due to different etiologies or pathogenic processes is not known. Furthermore, a specific underlying immunologic basis for these reactions has not been identified. Upon the appearance of rash or of other possibly allergic phenomena for which an alternative etiology cannot be identified, fluoxetine should be discontinued.

5.4 Screening Patients for Bipolar Disorder and Monitoring for Mania/Hypomania

A major depressive episode may be the initial presentation of Bipolar Disorder. It is generally believed (though not established in controlled trials) that treating such an episode with an antidepressant alone may increase the likelihood of precipitation of a mixed/manic episode in patients at risk for Bipolar Disorder. Whether any of the symptoms described for clinical worsening and suicide risk represent such a conversion is unknown. However, prior to initiating treatment with an antidepressant, patients with depressive symptoms should be adequately screened to determine if they are at risk for Bipolar Disorder; such screening should include a detailed psychiatric history, including a family history of suicide, Bipolar Disorder, and depression. Fluoxetine monotherapy is not indicated for the treatment of depressive episodes associated with Bipolar I Disorder.

In US placebo-controlled clinical trials for MDD, mania/hypomania was reported in 0.1% of patients treated with fluoxetine and 0.1% of patients treated with placebo. Activation of mania/hypomania has also been reported in a small proportion of patients with Major Affective Disorder treated with other marketed drugs effective in the treatment of MDD [see Use in Specific Populations (8.4)].

In US placebo-controlled clinical trials for OCD, mania/hypomania was reported in 0.8% of patients treated with fluoxetine and no patients treated with placebo. No patients reported mania/hypomania in US placebo-controlled clinical trials for bulimia. In US fluoxetine clinical trials, 0.7% of 10,782 patients reported mania/hypomania [see Use in Specific Populations (8.4)].

5.5 Seizures

In US placebo-controlled clinical trials for MDD, convulsions (or reactions described as possibly having been seizures) were reported in 0.1% of patients treated with fluoxetine and 0.2% of patients treated with placebo. No patients reported convulsions in US placebo-controlled clinical trials for either OCD or bulimia. In US fluoxetine clinical trials, 0.2% of 10,782 patients reported convulsions. The percentage appears to be similar to that associated with other marketed drugs effective in the treatment of MDD. Fluoxetine should be introduced with care in patients with a history of seizures. There have been rare reports of prolonged seizures in patients taking fluoxetine who are also receiving electroconvulsive therapy (ECT) treatment.

5.6 Altered Appetite and Weight

Significant weight loss, especially in underweight depressed or bulimic patients, may be an undesirable result of treatment with fluoxetine.

In US placebo-controlled clinical trials for MDD, 11% of patients treated with fluoxetine and 2% of patients treated with placebo reported anorexia (decreased appetite). Weight loss was reported in 1.4% of patients treated with fluoxetine and in 0.5% of patients treated with placebo. However, only rarely have patients discontinued treatment with fluoxetine because of anorexia or weight loss [see Use in Specific Populations (8.4)].

In US placebo-controlled clinical trials for OCD, 17% of patients treated with fluoxetine and 10% of patients treated with placebo reported anorexia (decreased appetite). One patient discontinued treatment with fluoxetine because of anorexia [see Use in Specific Populations (8.4)].

In US placebo-controlled clinical trials for Bulimia Nervosa, 8% of patients treated with fluoxetine 60 mg and 4% of patients treated with placebo reported anorexia (decreased appetite). Patients treated with fluoxetine 60 mg on average lost 0.45 kg compared with a gain of 0.16 kg by patients treated with placebo in the 16-week double-blind trial. Weight change should be monitored during therapy.

5.7 Increased Risk of Bleeding

SNRIs and SSRIs, including fluoxetine, may increase the risk of bleeding reactions. Concomitant use of aspirin, nonsteroidal anti-inflammatory drugs, warfarin, and other anti coagulants may add to this risk. Case reports and epidemiological studies (case-control and cohort design) have demonstrated an association between use of drugs that interfere with serotonin reuptake and the occurrence of gastrointestinal bleeding. Based on data from the published observational studies, exposure to SSRIs, particularly in the month before delivery, has been associated with a less than 2-fold increase in the risk of postpartum hemorrhage [see Use in Specific Populations (8.1)]. Bleeding reactions related to SNRIs and SSRIs use have ranged from ecchymoses, hematomas, epistaxis, and petechiae to life-threatening hemorrhages.

Patients should be cautioned about the increased risk of bleeding associated with the concomitant use of fluoxetine and NSAIDs, aspirin, warfarin, or other drugs that affect coagulation [see Drug Interactions (7.4)].

5.8 Angle-closure Glaucoma

The pupillary dilation that occurs following use of many antidepressant drugs including fluoxetine may trigger an angle closure attack in a patient with anatomically narrow angles who does not have a patent iridectomy.

5.9 Hyponatremia

Hyponatremia has been reported during treatment with SNRIs and SSRIs, including fluoxetine. In many cases, this hyponatremia appears to be the result of the syndrome of inappropriate antidiuretic hormone secretion (SIADH). Cases with serum sodium lower than 110 mmol/L have been reported and appeared to be reversible when fluoxetine was discontinued. Elderly patients may be at greater risk of developing hyponatremia with SNRIs and SSRIs. Also, patients taking diuretics or who are otherwise volume-depleted may be at greater risk [see Use in Specific Populations (8.5)]. Discontinuation of fluoxetine should be considered in patients with symptomatic hyponatremia and appropriate medical intervention should be instituted.

Signs and symptoms of hyponatremia include headache, difficulty concentrating, memory impairment, confusion, weakness, and unsteadiness, which may lead to falls. More severe and/or acute cases have been associated with hallucination, syncope, seizure, coma, respiratory arrest, and death.

5.10 Anxiety and Insomnia

In US placebo-controlled clinical trials for MDD, 12% to 16% of patients treated with fluoxetine and 7% to 9% of patients treated with placebo reported anxiety, nervousness, or insomnia.

In US placebo-controlled clinical trials for OCD, insomnia was reported in 28% of patients treated with fluoxetine and in 22% of patients treated with placebo. Anxiety was reported in 14% of patients treated with fluoxetine and in 7% of patients treated with placebo.

In US placebo-controlled clinical trials for Bulimia Nervosa, insomnia was reported in 33% of patients treated with fluoxetine 60 mg, and 13% of patients treated with placebo. Anxiety and nervousness were reported, respectively, in 15% and 11% of patients treated with fluoxetine 60 mg and in 9% and 5% of patients treated with placebo.

Among the most common adverse reactions associated with discontinuation (incidence at least twice that for placebo and at least 1% for fluoxetine in clinical trials collecting only a primary reaction associated with discontinuation) in US placebo-controlled fluoxetine clinical trials were anxiety (2% in OCD), insomnia (1% in combined indications and 2% in bulimia), and nervousness (1% in MDD) [Table 4].

5.11 QT Prolongation

Postmarketing cases of QT interval prolongation and ventricular arrhythmia including Torsades de Pointes have been reported in patients treated with fluoxetine. Fluoxetine should be used with caution in patients with congenital long QT syndrome; a previous history of QT prolongation; a family history of long QT syndrome or sudden cardiac death; and other conditions that predispose to QT prolongation and ventricular arrhythmia. Such conditions include concomitant use of drugs that prolong the QT interval; hypokalemia or hypomagnesemia; recent myocardial infarction, uncompensated heart failure, bradyarrhythmias, and other significant arrhythmias; and conditions that predispose to increased fluoxetine exposure (overdose, hepatic impairment, use of CYP2D6 inhibitors, CYP2D6 poor metabolizer status, or use of other highly protein-bound drugs). Fluoxetine is primarily metabolized by CYP2D6 [see Contraindications (4.2), Drug Interactions (7.6, 7.7), Overdosage (10), and Clinical Pharmacology (12.3)].

Pimozide and thioridazine are contraindicated for use with fluoxetine. Avoid the concomitant use of drugs known to prolong the QT interval. These include specific antipsychotics (e.g., ziprasidone, iloperidone, chlorpromazine, mesoridazine, droperidol); specific antibiotics (e.g., erythromycin, gatifloxacin, moxifloxacin, sparfloxacin); Class IA antiarrhythmic medications (e.g., quinidine, procainamide); Class III antiarrhythmics (e.g., amiodarone, sotalol); and others (e.g., pentamidine, levomethadyl acetate, methadone, halofantrine, mefloquine, dolasetron mesylate, probucol or tacrolimus) [see Drug Interactions (7.6, 7.7) and Clinical Pharmacology (12.3)].

Consider ECG assessment and periodic ECG monitoring if initiating treatment with fluoxetine in patients with risk factors for QT prolongation and ventricular arrhythmia. Consider discontinuing fluoxetine and obtaining a cardiac evaluation if patients develop signs or symptoms consistent with ventricular arrhythmia.

5.12 Use in Patients with Concomitant Illness

Clinical experience with fluoxetine in patients with concomitant systemic illness is limited. Caution is advisable in using fluoxetine in patients with diseases or conditions that could affect metabolism or hemodynamic responses.

Cardiovascular—Fluoxetine has not been evaluated or used to any appreciable extent in patients with a recent history of myocardial infarction or unstable heart disease. Patients with these diagnoses were systematically excluded from clinical studies during the product’s premarket testing. However, the ECGs of 312 patients who received fluoxetine in double-blind trials were retrospectively evaluated; no conduction abnormalities that resulted in heart block were observed. The mean heart rate was reduced by approximately 3 beats/min.

Glycemic Control—In patients with diabetes, fluoxetine may alter glycemic control. Hypoglycemia has occurred during therapy with fluoxetine, and hyperglycemia has developed following discontinuation of the drug. As is true with many other types of medication when taken concurrently by patients with diabetes, insulin and/or oral hypoglycemic, dosage may need to be adjusted when therapy with fluoxetine is instituted or discontinued.

5.13 Potential for Cognitive and Motor Impairment

As with any CNS-active drug, fluoxetine has the potential to impair judgment, thinking, or motor skills. Patients should be cautioned about operating hazardous machinery, including automobiles, until they are reasonably certain that the drug treatment does not affect them adversely.

5.14 Long Elimination Half-Life

Because of the long elimination half-lives of the parent drug and its major active metabolite, changes in dose will not be fully reflected in plasma for several weeks, affecting both strategies for titration to final dose and withdrawal from treatment. This is of potential consequence when drug discontinuation is required or when drugs are prescribed that might interact with fluoxetine and norfluoxetine following the discontinuation of fluoxetine [see Clinical Pharmacology (12.3)].

5.15 Discontinuation Adverse Reactions

During marketing of fluoxetine, SNRIs, and SSRIs, there have been spontaneous reports of adverse reactions occurring upon discontinuation of these drugs, particularly when abrupt, including the following: dysphoric mood, irritability, agitation, dizziness, sensory disturbances (e.g., paresthesias such as electric shock sensations), anxiety, confusion, headache, lethargy, emotional lability, insomnia, and hypomania. While these reactions are generally self-limiting, there have been reports of serious discontinuation symptoms. Patients should be monitored for these symptoms when discontinuing treatment with fluoxetine. A gradual reduction in the dose rather than abrupt cessation is recommended whenever possible. If intolerable symptoms occur following a decrease in the dose or upon discontinuation of treatment, then resuming the previously prescribed dose may be considered. Subsequently, the physician may continue decreasing the dose but at a more gradual rate. Plasma fluoxetine and norfluoxetine concentration decrease gradually at the conclusion of therapy which may minimize the risk of discontinuation symptoms with this drug.

5.16 Sexual Dysfunction

Use of SSRIs, including fluoxetine, may cause symptoms of sexual dysfunction [see Adverse Reactions (6.1)]. In male patients, SSRI use may result in ejaculatory delay or failure, decreased libido, and erectile dysfunction. In female patients, SSRI use may result in decreased libido and delayed or absent orgasm.

It is important for prescribers to inquire about sexual function prior to initiation of fluoxetine and to inquire specifically about changes in sexual function during treatment, because sexual function may not be spontaneously reported. When evaluating changes in sexual function, obtaining a detailed history (including timing of symptom onset) is important because sexual symptoms may have other causes, including the underlying psychiatric disorder. Discuss potential management strategies to support patients in making informed decisions about treatment.

6 ADVERSE REACTIONS

The following adverse reactions are discussed in more detail in other sections of the labeling:

- Suicidal Thoughts and Behaviors in Children, Adolescents, and Young Adults [see Boxed Warning and Warnings and Precautions (5.1)]
- Serotonin Syndrome [see Warnings and Precautions (5.2)]
- Allergic Reactions and Rash [see Warnings and Precautions (5.3)]
- Screening Patients for Bipolar Disorder and Monitoring for Mania/Hypomania [see Warnings and Precautions (5.4)]
- Seizures [see Warnings and Precautions (5.5)]
- Altered Appetite and Weight [see Warnings and Precautions (5.6)]
- Increased Risk of Bleeding [see Warnings and Precautions (5.7)]
- Angle-closure Glaucoma [see Warnings and Precautions (5.8)]
- Hyponatremia [see Warnings and Precautions (5.9)]
- Anxiety and Insomnia [see Warnings and Precautions (5.10)]
- QT Prolongation [see Warnings and Precautions (5.11)]
- Potential for Cognitive and Motor Impairment [see Warnings and Precautions (5.13)]
- Discontinuation Adverse Reactions [see Warnings and Precautions (5.15)]

6.1 Clinical Trials Experience

Because clinical trials are conducted under widely varying conditions, adverse reaction rates observed in the clinical trials of a drug cannot be directly compared to rates in the clinical trials of another drug and may not reflect or predict the rates observed in practice.

Multiple doses of fluoxetine have been administered to 10,782 patients with various diagnoses in US clinical trials. In addition, there have been 425 patients administered fluoxetine in panic clinical trials. The stated frequencies represent the proportion of individuals who experienced, at least once, an adverse reaction of the type listed. An adverse reaction was included if it occurred for the first time or worsened while receiving therapy following baseline evaluation.

Incidence in MDD, OCD, Bulimia, and Panic Disorder placebo-controlled clinical trials (excluding data from extensions of trials)—Table 2 enumerates the most common adverse reactions associated with the use of fluoxetine (incidence of at least 5% for fluoxetine and at least twice that for placebo within at least 1 of the indications) for the treatment of MDD, OCD, and bulimia in US controlled clinical trials and Panic Disorder in US plus non-US controlled trials. Table 3 provides combined data for the pool of studies that are provided separately by indication in Table 2 .

Table 2. Most Common Adverse Reactions: Incidence in Major Depressive Disorder, Obsessive Compulsive Disorder, Bulimia, and Panic Disorder Placebo-controlled Clinical Trials
 | Percentage of Patients Reporting Event
 | MDD |  | OCD |  | Bulimia |  | Panic Disorder
Body System/ Adverse Reaction | Fluoxetine (N = 1728) | Placebo (N = 975) | Fluoxetine (N = 266) | Placebo (N = 89) | Fluoxetine (N = 450) | Placebo (N = 267) | Fluoxetine (N = 425) | Placebo (N = 342)
Body as a Whole
Asthenia | 9 | 5 | 15 | 11 | 21 | 9 | 7 | 7
Flu syndrome | 3 | 4 | 10 | 7 | 8 | 3 | 5 | 5
Cardiovascular System
Vasodilatation | 3 | 2 | 5 | -- | 2 | 1 | 1 | --
Digestive System
Nausea | 21 | 9 | 26 | 13 | 29 | 11 | 12 | 7
Diarrhea | 12 | 8 | 18 | 13 | 8 | 6 | 9 | 4
Anorexia | 11 | 2 | 17 | 10 | 8 | 4 | 4 | 1
Dry mouth | 10 | 7 | 12 | 3 | 9 | 6 | 4 | 4
Dyspepsia | 7 | 5 | 10 | 4 | 10 | 6 | 6 | 2
Nervous System
Insomnia | 16 | 9 | 28 | 22 | 33 | 13 | 10 | 7
Anxiety | 12 | 7 | 14 | 7 | 15 | 9 | 6 | 2
Nervousness | 14 | 9 | 14 | 15 | 11 | 5 | 8 | 6
Somnolence | 13 | 6 | 17 | 7 | 13 | 5 | 5 | 2
Tremor | 10 | 3 | 9 | 1 | 13 | 1 | 3 | 1
Libido decreased | 3 | -- | 11 | 2 | 5 | 1 | 1 | 2
Abnormal dreams | 1 | 1 | 5 | 2 | 5 | 3 | 1 | 1
Respiratory System
Pharyngitis | 3 | 3 | 11 | 9 | 10 | 5 | 3 | 3
Sinusitis | 1 | 4 | 5 | 2 | 6 | 4 | 2 | 3
Yawn | -- | -- | 7 | -- | 11 | -- | 1 | --
Skin and Appendages
Sweating | 8 | 3 | 7 | -- | 8 | 3 | 2 | 2
Rash | 4 | 3 | 6 | 3 | 4 | 4 | 2 | 2
Urogenital System
Impotencea | 2 | -- | -- | -- | 7 | -- | 1 | --
Abnormal ejaculationa | -- | -- | 7 | -- | 7 | -- | 2 | 1
Note: Includes US data for MDD, OCD, Bulimia, and Panic Disorder clinical trials, plus non-US data for Panic Disorder clinical trials.
a = Denominator used was for males only (N = 690 fluoxetine MDD; N = 410 placebo MDD; N = 116 fluoxetine OCD; N = 43 placebo OCD; N = 14 fluoxetine Bulimia; N = 1 placebo Bulimia; N = 162 fluoxetine Panic Disorder; N = 121 placebo Panic Disorder).
-- = Incidence less than 1%.

Table 3. Adverse Reactions: Incidence in Major Depressive Disorder, Obsessive Compulsive Disorder, Bulimia, and Panic Disorder Placebo-controlled Clinical Trials
 | Percentage of Patients Reporting Event
 | MDD, OCD, Bulimia, and Panic Disorder Combined
Body System/Adverse Reaction | Fluoxetine (N = 2869) | Placebo (N = 1673)
Body as a Whole
Headache | 21 | 19
Asthenia | 11 | 6
Flu syndrome | 5 | 4
Fever | 2 | 1
Cardiovascular System
Vasodilatation | 2 | 1
Digestive System
Nausea | 22 | 9
Diarrhea | 11 | 7
Anorexia | 10 | 3
Dry mouth | 9 | 6
Dyspepsia | 8 | 4
Constipation | 5 | 4
Flatulence | 3 | 2
Vomiting | 3 | 2
Metabolic and Nutritional Disorders
Weight loss | 2 | 1
Nervous System
Insomnia | 19 | 10
Nervousness | 13 | 8
Anxiety | 12 | 6
Somnolence | 12 | 5
Dizziness | 9 | 6
Tremor | 9 | 2
Libido decreased | 4 | 1
Thinking abnormal | 2 | 1
Respiratory System
Yawn | 3 | --
Skin and Appendages
Sweating | 7 | 3
Rash | 4 | 3
Pruritus | 3 | 2
Special Senses
Abnormal vision | 2 | 1
Note: Includes US data for MDD, OCD, Bulimia, and Panic Disorder clinical trials, plus non-US data for Panic Disorder clinical trials.
-- = Incidence less than 1%.

Associated with discontinuation in MDD, OCD, Bulimia, and Panic Disorder placebo-controlled clinical trials (excluding data from extensions of trials)—Table 4 lists the adverse reactions associated with discontinuation of fluoxetine treatment (incidence at least twice that for placebo and at least 1% for fluoxetine in clinical trials collecting only a primary reaction associated with discontinuation) in MDD, OCD, Bulimia, and Panic Disorder clinical trials, plus non-US Panic Disorder clinical trials.

Table 4. Most Common Adverse Reactions Associated with Discontinuation in Major Depressive Disorder, Obsessive Compulsive Disorder, Bulimia, and Panic Disorder Placebo-controlled Clinical Trials
MDD, OCD, Bulimia, and Panic Disorder Combined (N = 1533) | MDD (N = 392) | OCD (N = 266) | Bulimia (N = 450) | Panic Disorder (N = 425)
Anxiety (1%) | -- | Anxiety (2%) | -- | Anxiety (2%)
-- | -- | -- | Insomnia (2%) | --
-- | Nervousness (1%) | -- | -- | Nervousness (1%)
-- | -- | Rash (1%) | -- | --
Note: Includes US data for MDD, OCD, Bulimia, and Panic Disorder clinical trials, plus non-US data for Panic Disorder clinical trials.
-- = Incidence less than 1%.

Other adverse reactions in pediatric patients (children and adolescents)—Adverse reactions were collected in 322 pediatric patients (180 fluoxetine-treated, 142 placebo-treated). The overall profile of adverse reactions was generally similar to that seen in adult studies, as shown in Table 2 and Table 3. However, the following adverse reactions (excluding those which appear in the body or footnotes of Table 2 and Table 3 and those for which the COSTART terms were uninformative or misleading) were reported at an incidence of at least 2% for fluoxetine and greater than placebo: thirst, hyperkinesia, agitation, personality disorder, epistaxis, urinary frequency, and menorrhagia.

The most common adverse reaction (incidence at least 1% for fluoxetine and greater than placebo) associated with discontinuation in 3 pediatric placebo-controlled trials (N = 418 randomized; 228 fluoxetine-treated; 190 placebo-treated) was mania/hypomania (1.8% for fluoxetine-treated, 0% for placebo-treated). In these clinical trials, only a primary reaction associated with discontinuation was collected.

Male and female sexual dysfunction with SSRIs—Although changes in sexual desire, sexual performance, and sexual satisfaction often occur as manifestations of a psychiatric disorder, they may also be a consequence of pharmacologic treatment. In particular, some evidence suggests that SSRIs can cause such untoward sexual experiences. Reliable estimates of the incidence and severity of untoward experiences involving sexual desire, performance, and satisfaction are difficult to obtain, however, in part because patients and physicians may be reluctant to discuss them. Accordingly, estimates of the incidence of untoward sexual experience and performance, cited in product labeling, are likely to underestimate their actual incidence. In patients enrolled in US MDD, OCD, and bulimia placebo-controlled clinical trials, decreased libido was the only sexual adverse reaction reported by at least 2% of patients taking fluoxetine (4% fluoxetine, < 1% placebo). There have been spontaneous reports in women taking fluoxetine of orgasmic dysfunction, including anorgasmia.

There are no adequate and well-controlled studies examining sexual dysfunction with fluoxetine treatment.

Symptoms of sexual dysfunction occasionally persist after discontinuation of fluoxetine treatment.

Priapism has been reported with all SSRIs.

While it is difficult to know the precise risk of sexual dysfunction associated with the use of SSRIs, physicians should routinely inquire about such possible adverse reactions.

Other adverse reactions observed during the premarketing evaluation of fluoxetine—Following is a list of adverse reactions reported by patients treated with fluoxetine in clinical trials. This listing is not intended to include reactions (1) already listed in previous tables or elsewhere in labeling, (2) for which a drug cause was remote, (3) which were so general as to be uninformative, (4) which were not considered to have significant clinical implications, or (5) which occurred at a rate equal to or less than placebo.

Reactions are classified by body system using the following definitions: frequent adverse reactions are those occurring in at least 1/100 patients; infrequent adverse reactions are those occurring in 1/100 to 1/1000 patients; rare reactions are those occurring in fewer than 1/1000 patients.

Body as a Whole—Frequent: chills; Infrequent: suicide attempt; Rare: acute abdominal syndrome, photosensitivity reaction.

Cardiovascular System—Frequent: palpitation; Infrequent: arrhythmia, hypotension^1.

Digestive System—Infrequent: dysphagia, gastritis, gastroenteritis, melena, stomach ulcer; Rare: bloody diarrhea, duodenal ulcer, esophageal ulcer, gastrointestinal hemorrhage, hematemesis, hepatitis, peptic ulcer, stomach ulcer hemorrhage.

Hemic and Lymphatic System—Infrequent: ecchymosis; Rare: petechia, purpura.

Nervous System—Frequent: emotional lability; Infrequent: akathisia, ataxia, balance disorder^1, bruxism^1, buccoglossal syndrome, depersonalization, euphoria, hypertonia, libido increased, myoclonus, paranoid reaction; Rare: delusions.

Respiratory System—Rare: larynx edema.

Skin and Appendages—Infrequent: alopecia; Rare: purpuric rash.

Special Senses—Frequent: taste perversion; Infrequent: mydriasis.

Urogenital System—Frequent: micturition disorder; Infrequent: dysuria, gynecological bleeding^2.

^1MedDRA dictionary term from integrated database of placebo-controlled trials of 15,870 patients, of which 9,673 received fluoxetine.

^2Group term that includes individual MedDRA terms: cervix hemorrhage uterine, dysfunctional uterine bleeding, genital hemorrhage, menometrorrhagia, menorrhagia, metrorrhagia, polymenorrhea, postmenopausal hemorrhage, uterine hemorrhage, vaginal hemorrhage. Adjusted for gender.

6.2 Postmarketing Experience

The following adverse reactions have been identified during postapproval use of fluoxetine. Because these reactions are reported voluntarily from a population of uncertain size, it is difficult to reliably estimate their frequency or evaluate a causal relationship to drug exposure.

Voluntary reports of adverse reactions temporally associated with fluoxetine that have been received since market introduction and that may have no causal relationship with the drug include the following: anosmia, aplastic anemia, atrial fibrillation^1, cataract, cerebrovascular accident^1, cholestatic jaundice, drug reaction with eosinophilia and systemic symptoms (DRESS), dyskinesia (including, for example, a case of buccal-lingual-masticatory syndrome with involuntary tongue protrusion reported to develop in a 77-year-old female after 5 weeks of fluoxetine therapy and which completely resolved over the next few months following drug discontinuation), eosinophilic pneumonia^1, epidermal necrolysis, erythema multiforme, erythema nodosum, exfoliative dermatitis, galactorrhea, gynecomastia, heart arrest^1, hepatic failure/necrosis, hyperprolactinemia, hypoglycemia, hyposmia, immune-related hemolytic anemia, kidney failure, memory impairment, movement disorders developing in patients with risk factors including drugs associated with such reactions and worsening of preexisting movement disorders, optic neuritis, pancreatitis^1, pancytopenia, pulmonary embolism, pulmonary hypertension, QT prolongation, Stevens-Johnson syndrome, thrombocytopenia^1, thrombocytopenic purpura, ventricular tachycardia (including Torsades de Pointes-type arrhythmias), vaginal bleeding, and violent behaviors^1.

^1These terms represent serious adverse events, but do not meet the definition for adverse drug reactions. They are included here because of their seriousness.

7 DRUG INTERACTIONS

As with all drugs, the potential for interaction by a variety of mechanisms (e.g., pharmacodynamic, pharmacokinetic drug inhibition or enhancement, etc.) is a possibility.

7.1 Monoamine Oxidase Inhibitors (MAOIs)

[See Dosage and Administration (2.6, 2.7), Contraindications (4.1), and Warnings and Precautions (5.2)].

7.2 CNS Acting Drugs

Caution is advised if the concomitant administration of fluoxetine and such drugs is required. In evaluating individual cases, consideration should be given to using lower initial doses of the concomitantly administered drugs, using conservative titration schedules, and monitoring of clinical status [see Clinical Pharmacology (12.3)].

7.3 Other Serotonergic Drugs

The concomitant use of serotonergic drugs (including other SSRIs, SNRIs, triptans, tricyclic antidepressants, opioids, lithium, buspirone, amphetamines, tryptophan, and St. John's Wort) with fluoxetine increases the risk of serotonin syndrome. Monitor patients for signs and symptoms of serotonin syndrome, particularly during treatment initiation and dosage increases. If serotonin syndrome occurs, consider discontinuation of fluoxetine and/or concomitant serotonergic drugs [see Warnings and Precautions (5.2)].

7.4 Drugs that Interfere with Hemostasis (e.g., NSAIDS, Aspirin, Warfarin)

Serotonin release by platelets plays an important role in hemostasis. Epidemiological studies of the case-control and cohort design that have demonstrated an association between use of psychotropic drugs that interfere with serotonin reuptake and the occurrence of upper gastrointestinal bleeding have also shown that concurrent use of an NSAID or aspirin may potentiate this risk of bleeding. Altered anticoagulant effects, including increased bleeding, have been reported when SNRIs or SSRIs are co-administered with warfarin. Patients receiving warfarin therapy should be carefully monitored when fluoxetine is initiated or discontinued [see Warnings and Precautions (5.7)].

7.5 Potential for Other Drugs to Affect Fluoxetine

Drugs tightly bound to plasma proteins—Because fluoxetine is tightly bound to plasma proteins, adverse effects may result from displacement of protein-bound fluoxetine by other tightly bound drugs [see Clinical Pharmacology (12.3)].

7.6 Potential for Fluoxetine to Affect Other Drugs

Pimozide—Concomitant use in patients taking pimozide is contraindicated. Pimozide can prolong the QT interval. Fluoxetine can increase the level of pimozide through inhibition of CYP2D6. Fluoxetine can also prolong the QT interval. Clinical studies of pimozide with other antidepressants demonstrate an increase in drug interaction or QT prolongation. While a specific study with pimozide and fluoxetine has not been conducted, the potential for drug interactions or QT prolongation warrants restricting the concurrent use of pimozide and fluoxetine [see Contraindications (4.2), Warnings and Precautions (5.11), and Drug Interactions (7.7)].

Thioridazine—Thioridazine should not be administered with fluoxetine or within a minimum of 5 weeks after fluoxetine has been discontinued, because of the risk of QT prolongation [see Contraindications (4.2), Warnings and Precautions (5.11), and Drug Interactions (7.7)].

In a study of 19 healthy male subjects, which included 6 slow and 13 rapid hydroxylators of debrisoquin, a single 25-mg oral dose of thioridazine produced a 2.4-fold higher Cmax and a 4.5-fold higher area under the curve (AUC) for thioridazine in the slow hydroxylators compared with the rapid hydroxylators. The rate of debrisoquin hydroxylation is felt to depend on the level of CYP2D6 isozyme activity. Thus, this study suggests that drugs which inhibit CYP2D6, such as certain SSRIs, including fluoxetine, will produce elevated plasma levels of thioridazine.

Thioridazine administration produces a dose-related prolongation of the QT interval, which is associated with serious ventricular arrhythmias, such as Torsades de Pointes-type arrhythmias, and sudden death. This risk is expected to increase with fluoxetine-induced inhibition of thioridazine metabolism.

Drugs metabolized by CYP2D6—Fluoxetine inhibits the activity of CYP2D6, and may make individuals with normal CYP2D6 metabolic activity resemble a poor metabolizer. Co-administration of fluoxetine with other drugs that are metabolized by CYP2D6, including certain antidepressants (e.g., TCAs), antipsychotics (e.g., phenothiazines and most atypicals), and antiarrhythmics (e.g., propafenone, flecainide, and others) should be approached with caution. Therapy with medications that are predominantly metabolized by the CYP2D6 system and that have a relatively narrow therapeutic index (see list below) should be initiated at the low end of the dose range if a patient is receiving fluoxetine concurrently or has taken it in the previous 5 weeks. Thus, his/her dosing requirements resemble those of poor metabolizers. If fluoxetine is added to the treatment regimen of a patient already receiving a drug metabolized by CYP2D6, the need for decreased dose of the original medication should be considered. Drugs with a narrow therapeutic index represent the greatest concern (e.g., flecainide, propafenone, vinblastine, and TCAs). Due to the risk of serious ventricular arrhythmias and sudden death potentially associated with elevated plasma levels of thioridazine, thioridazine should not be administered with fluoxetine or within a minimum of 5 weeks after fluoxetine has been discontinued [see Contraindications (4.2)].

Tricyclic antidepressants (TCAs)—In 2 studies, previously stable plasma levels of imipramine and desipramine have increased greater than 2- to 10-fold when fluoxetine has been administered in combination. This influence may persist for 3 weeks or longer after fluoxetine is discontinued. Thus, the dose of TCAs may need to be reduced and plasma TCA concentrations may need to be monitored temporarily when fluoxetine is co-administered or has been recently discontinued [see Warnings and Precautions (5.2) and Clinical Pharmacology (12.3)].

Benzodiazepines—The half-life of concurrently administered diazepam may be prolonged in some patients [see Clinical Pharmacology (12.3)]. Co-administration of alprazolam and fluoxetine has resulted in increased alprazolam plasma concentrations and in further psychomotor performance decrement due to increased alprazolam levels.

Antipsychotics—Some clinical data suggests a possible pharmacodynamic and/or pharmacokinetic interaction between SSRIs and antipsychotics. Elevation of blood levels of haloperidol and clozapine has been observed in patients receiving concomitant fluoxetine.

Anticonvulsants—Patients on stable doses of phenytoin and carbamazepine have developed elevated plasma anticonvulsant concentrations and clinical anticonvulsant toxicity following initiation of concomitant fluoxetine treatment.

Lithium—There have been reports of both increased and decreased lithium levels when lithium was used concomitantly with fluoxetine. Cases of lithium toxicity and increased serotonergic effects have been reported. Lithium levels should be monitored when these drugs are administered concomitantly [see Warnings and Precautions (5.2)].

Drugs tightly bound to plasma proteins—Because fluoxetine is tightly bound to plasma proteins, the administration of fluoxetine to a patient taking another drug that is tightly bound to protein (e.g., Coumadin, digitoxin) may cause a shift in plasma concentrations potentially resulting in an adverse effect [see Clinical Pharmacology (12.3)].

Drugs metabolized by CYP3A4—In an in vivo interaction study involving co-administration of fluoxetine with single doses of terfenadine (a CYP3A4 substrate), no increase in plasma terfenadine concentrations occurred with concomitant fluoxetine.

Additionally, in vitro studies have shown ketoconazole, a potent inhibitor of CYP3A4 activity, to be at least 100 times more potent than fluoxetine or norfluoxetine as an inhibitor of the metabolism of several substrates for this enzyme, including astemizole, cisapride, and midazolam. These data indicate that fluoxetine’s extent of inhibition of CYP3A4 activity is not likely to be of clinical significance.

Olanzapine—Fluoxetine (60 mg single dose or 60 mg daily dose for 8 days) causes a small (mean 16%) increase in the maximum concentration of olanzapine and a small (mean 16%) decrease in olanzapine clearance. The magnitude of the impact of this factor is small in comparison to the overall variability between individuals, and therefore dose modification is not routinely recommended.

7.7 Drugs That Prolong the QT Interval

Do not use fluoxetine in combination with thioridazine or pimozide. Use fluoxetine with caution in combination with other drugs that cause QT prolongation. These include: specific antipsychotics (e.g., ziprasidone, iloperidone, chlorpromazine, mesoridazine, droperidol); specific antibiotics (e.g., erythromycin, gatifloxacin, moxifloxacin, sparfloxacin); Class IA antiarrhythmic medications (e.g., quinidine, procainamide); Class III antiarrhythmics (e.g., amiodarone, sotalol); and others (e.g., pentamidine, levomethadyl acetate, methadone, halofantrine, mefloquine, dolasetron mesylate, probucol or tacrolimus). Fluoxetine is primarily metabolized by CYP2D6. Concomitant treatment with CYP2D6 inhibitors can increase the concentration of fluoxetine. Concomitant use of other highly protein-bound drugs can increase the concentration of fluoxetine [see Contraindications (4.2), Warnings and Precautions (5.11), Drug Interactions (7.6), and Clinical Pharmacology (12.3)].

8 USE IN SPECIFIC POPULATIONS

8.1 Pregnancy

Pregnancy Exposure Registry

There is a pregnancy exposure registry that monitors pregnancy outcomes in women exposed to antidepressants during pregnancy. Healthcare providers are encouraged to register patients by calling the National Pregnancy Registry for Antidepressants at 1-866-961-2388 or visiting online at https://womensmentalhealth.org/research/pregnancyregistry/antidepressants/.

Risk Summary

Based on data from published observational studies, exposure to SSRIs, particularly in the month before delivery, has been associated with a less than 2-fold increase in the risk of postpartum hemorrhage [see Warnings and Precautions (5.7) and Clinical Considerations].

Available data from published epidemiologic studies and postmarketing reports over several decades have not established an increased risk of major birth defects or miscarriage. Some studies have reported an increased incidence of cardiovascular malformations; however, these studies results do not establish a causal relationship (see Data). There are risks associated with untreated depression in pregnancy and risks of persistent pulmonary hypertension of the newborn (PPHN) (see Data) and poor neonatal adaptation with exposure to selective serotonin reuptake inhibitors (SSRIs), including Fluoxetine Tablets, during pregnancy (see Clinical Considerations).

In rats and rabbits treated with fluoxetine during the period of organogenesis, there was no evidence of developmental effects at doses up to 1.6 and 3.9 times, respectively, the maximum recommended human dose (MRHD) of 60 mg on a mg/m^2 given to adolescents on a mg/m^2 basis. However, in other reproductive studies in rats, an increase in stillborn pups, a decrease in pup weight, and an increase in pup deaths early after birth occurred at doses that are 1.5 times (during gestation) and 0.97 times (during gestation and lactation) the MRHD given to adolescents on a mg/m^2 basis.

The estimated background risk of major birth defects and miscarriage for the indicated population is unknown. All pregnancies have a background risk of birth defect, loss, or other adverse outcomes. In the US general population, the estimated background risk of major birth defects and miscarriage in clinically recognized pregnancies is 2% to 4% and 15% to 20%, respectively.

Clinical Considerations

Disease-Associated Maternal and/or Embryo/Fetal Risk

Women who discontinue antidepressants during pregnancy are more likely to experience a relapse of major depression than women who continue antidepressants. This finding is from a prospective, longitudinal study that followed 201 pregnant women with a history of major depressive disorder who were euthymic and taking antidepressants at the beginning of pregnancy. Consider the risk of untreated depression when discontinuing or changing treatment with antidepressant medication during pregnancy and postpartum.

Maternal Adverse Reactions

Use of Fluoxetine Tablets in the month before delivery may be associated with an increased risk of postpartum hemorrhage [see Warnings and Precautions (5.7)].

Fetal/Neonatal Adverse Reactions

Neonates exposed to Fluoxetine Tablets and other SSRIs or SNRIs late in the third trimester have developed complications requiring prolonged hospitalization, respiratory support, and tube feeding. Such complications can arise immediately upon delivery. Reported clinical findings have included respiratory distress, cyanosis, apnea, seizures, temperature instability, feeding difficulty, vomiting, hypoglycemia, hypotonia, hypertonia, hyperreflexia, tremors, jitteriness, irritability, and constant crying. These findings are consistent with either a direct toxic effect of SSRIs and SNRIs or possibly a drug discontinuation syndrome. It should be noted that, in some cases, the clinical picture is consistent with serotonin syndrome [see Warnings and Precautions (5.2)].

Data

Human Data

It has been shown that SSRIs (including fluoxetine) can cross the placenta. Published epidemiological studies of pregnant women exposed to fluoxetine have not established an increased risk of major birth defects, miscarriage, and other adverse developmental outcomes. Several publications reported an increased incidence of cardiovascular malformations in children with in utero exposure to fluoxetine. However, these studies results do not establish a causal relationship. Methodologic limitations of these observational studies include possible exposure and outcome misclassification, lack of adequate controls, adjustment for confounders and confirmatory studies. However, these studies cannot definitely establish or exclude any drug-associated risk during pregnancy.

Exposure to SSRIs, particularly later in pregnancy, may have an increased risk for PPHN. PPHN occurs in 1 to 2 per 1000 live births in the general population and is associated with substantial neonatal morbidity and mortality.

Animal data

In embryofetal development studies in rats and rabbits, there was no evidence of malformations or developmental variations following administration of fluoxetine at doses up to 12.5 and 15 mg/kg/day, respectively (1.6 and 3.9 times, respectively, the MRHD of 60 mg given to adolescents on a mg/m^2 basis) throughout organogenesis. However, in rat reproduction studies, an increase in stillborn pups, a decrease in pup weight, and an increase in pup deaths during the first 7 days postpartum occurred following maternal exposure to 12 mg/kg/day (1.5 times the MRHD given to adolescents on a mg/m^2 basis) during gestation or 7.5 mg/kg/day (0.97 times the MRHD given to adolescents on a mg/m^2 basis) during gestation and lactation. There was no evidence of developmental neurotoxicity in the surviving offspring of rats treated with 12 mg/kg/day during gestation. The no-effect dose for rat pup mortality was 5 mg/kg/day (0.65 times the MRHD given to adolescents on a mg/m^2 basis).

8.2 Lactation

Risk Summary

Data from published literature report the presence of fluoxetine and norfluoxetine in human milk (see Data). There are reports of agitation, irritability, poor feeding, and poor weight gain in infants exposed to fluoxetine through breast milk (see Clinical Considerations). There are no data on the effect of fluoxetine or its metabolites on milk production. The developmental and health benefits of breastfeeding should be considered along with the mother’s clinical need for Fluoxetine Tablets and any potential adverse effects on the breastfed child from Fluoxetine Tablets or the underlying maternal condition.

Clinical Considerations

Infants exposed to Fluoxetine Tablets should be monitored for agitation, irritability, poor feeding, and poor weight gain.

Data

A study of 19 nursing mothers on fluoxetine with daily doses of 10 to 60 mg showed that fluoxetine was detectable in 30% of nursing infant sera (range: 1 to 84 ng/mL) whereas norfluoxetine was found in 85% (range: <1 to 265 ng/mL).

8.4 Pediatric Use

Use of fluoxetine in children—The efficacy of fluoxetine for the treatment of MDD was demonstrated in two 8- to 9-week placebo-controlled clinical trials with 315 pediatric outpatients ages 8 to ≤ 18 [see Clinical Studies (14.1)].

The efficacy of fluoxetine for the treatment of OCD was demonstrated in one 13-week placebo-controlled clinical trial with 103 pediatric outpatients ages 7 to < 18 [see Clinical Studies (14.2)].

The safety and effectiveness in pediatric patients < 8 years of age in MDD and < 7 years of age in OCD have not been established.

Fluoxetine pharmacokinetics were evaluated in 21 pediatric patients (ages 6 to ≤ 18) with MDD or OCD [see Clinical Pharmacology (12.3)].

The acute adverse reaction profiles observed in the 3 studies (N = 418 randomized; 228 fluoxetine-treated, 190 placebo-treated) were generally similar to that observed in adult studies with fluoxetine. The longer-term adverse reaction profile observed in the 19-week MDD study (N = 219 randomized; 109 fluoxetine-treated, 110 placebo-treated) was also similar to that observed in adult trials with fluoxetine [see Adverse Reactions (6.1)].

Manic reaction, including mania and hypomania, was reported in 6 (1 mania, 5 hypomania) out of 228 (2.6%) fluoxetine-treated patients and in 0 out of 190 (0%) placebo-treated patients. Mania/hypomania led to the discontinuation of 4 (1.8%) fluoxetine-treated patients from the acute phases of the 3 studies combined. Consequently, regular monitoring for the occurrence of mania/hypomania is recommended.

As with other SSRIs, decreased weight gain has been observed in association with the use of fluoxetine in children and adolescent patients. After 19 weeks of treatment in a clinical trial, pediatric subjects treated with fluoxetine gained an average of 1.1 cm less in height and 1.1 kg less in weight than subjects treated with placebo. In addition, fluoxetine treatment was associated with a decrease in alkaline phosphatase levels. The safety of fluoxetine treatment for pediatric patients has not been systematically assessed for chronic treatment longer than several months in duration. In particular, there are no studies that directly evaluate the longer-term effects of fluoxetine on the growth, development, and maturation of children and adolescent patients. Therefore, height and weight should be monitored periodically in pediatric patients receiving fluoxetine [see Warnings and Precautions (5.6)].

Fluoxetine is approved for use in pediatric patients with MDD and OCD [see Boxed Warning and Warnings and Precautions (5.1)]. Anyone considering the use of fluoxetine in a child or adolescent must balance the potential risks with the clinical need.

Juvenile Animal Toxicity Data—Significant toxicity on muscle tissue, neurobehavior, reproductive organs, and bone development has been observed following exposure of juvenile rats to fluoxetine from weaning through maturity. Oral administration of fluoxetine to rats from weaning postnatal day 21 through adulthood day 90 at 3, 10, or 30 mg/kg/day was associated with testicular degeneration and necrosis, epididymal vacuolation, and hypospermia (at 30 mg/kg/day corresponding to plasma exposures [AUC] approximately 5 to 10 times the average AUC in pediatric patients at the MRHD of 20 mg/day); increased serum levels of creatine kinase (at AUC as low as 1 to 2 times the average AUC in pediatric patients at the MRHD of 20 mg/day); skeletal muscle degeneration and necrosis; decreased femur length/growth; and body weight gain (at AUC 5 to 10 times the average AUC in pediatric patients at the MRHD of 20 mg/day). The high dose of 30 mg/kg/day exceeded a maximum tolerated dose. When animals were evaluated after a drug-free period (up to 11 weeks after cessation of dosing), fluoxetine was associated with neurobehavioral abnormalities (decreased reactivity at AUC as low as approximately 0.1 to 0.2 times the average AUC in pediatric patients at the MRHD and learning deficit at the high dose) and reproductive functional impairment (decreased mating at all doses and impaired fertility at the high dose). In addition, the testicular and epididymal microscopic lesions and decreased sperm concentrations found in the high dose group were also observed, indicating that the drug effects on reproductive organs are irreversible. The reversibility of fluoxetine-induced muscle damage was not assessed.

These fluoxetine toxicities in juvenile rats have not been observed in adult animals. Plasma exposures (AUC) to fluoxetine in juvenile rats receiving 3, 10, or 30 mg/kg/day doses in this study are approximately 0.1 to 0.2, 1 to 2, and 5 to 10 times, respectively, the average exposure in pediatric patients receiving the MRHD of 20 mg/day. Rat exposures to the major metabolite, norfluoxetine, were approximately 0.3 to 0.8, 1 to 8, and 3 to 20 times, respectively, the pediatric exposure at the MRHD.

A specific effect on bone development was reported in juvenile mice administered fluoxetine by the intraperitoneal route to 4-week-old mice for 4 weeks at doses 0.5 and 2 times the oral MRHD of 20 mg/day on a mg/m^2 basis. There was a decrease in bone mineralization and density at both doses, but the overall growth (body weight gain or femur length) was not affected.

8.5 Geriatric Use

US fluoxetine clinical trials included 687 patients ≥ 65 years of age and 93 patients ≥ 75 years of age. The efficacy in geriatric patients has been established [see Clinical Studies (14.1)]. For pharmacokinetic information in geriatric patients, [see Clinical Pharmacology (12.3)]. No overall differences in safety or effectiveness were observed between these subjects and younger subjects, and other reported clinical experience has not identified differences in responses between the elderly and younger patients, but greater sensitivity of some older individuals cannot be ruled out. SNRIs and SSRIs, including fluoxetine, have been associated with cases of clinically significant hyponatremia in elderly patients, who may be at greater risk for this adverse reaction [see Warnings and Precautions (5.9)].

8.6 Hepatic Impairment

In subjects with cirrhosis of the liver, the clearances of fluoxetine and its active metabolite, norfluoxetine, were decreased, thus increasing the elimination half-lives of these substances. A lower or less frequent dose of fluoxetine should be used in patients with cirrhosis. Caution is advised when using fluoxetine in patients with diseases or conditions that could affect its metabolism [see Dosage and Administration (2.5) and Clinical Pharmacology (12.3)].

9 DRUG ABUSE AND DEPENDENCE

9.3 Dependence

Fluoxetine has not been systematically studied, in animals or humans, for its potential for abuse, tolerance, or physical dependence. While the premarketing clinical experience with fluoxetine did not reveal any tendency for a withdrawal syndrome or any drug-seeking behavior, these observations were not systematic and it is not possible to predict on the basis of this limited experience the extent to which a CNS-active drug will be misused, diverted, and/or abused once marketed. Consequently, physicians should carefully evaluate patients for history of drug abuse and follow such patients closely, observing them for signs of misuse or abuse of fluoxetine (e.g., development of tolerance, incrementation of dose, drug-seeking behavior).

10 OVERDOSAGE

The following have been reported with fluoxetine tablet overdosage:

- Seizures, which may be delayed, and altered mental status including coma.
- Cardiovascular toxicity, which may be delayed, including QRS and QTc interval prolongation, wide complex tachyarrhythmias, torsade de pointes, and cardiac arrest. Hypertension most commonly seen, but rarely can see hypotension alone or with co-ingestants including alcohol.
- Serotonin syndrome (patients with a multiple drug overdosage with other proserotonergic drugs may have a higher risk).

Gastrointestinal decontamination with activated charcoal should be considered in patients who present early after a fluoxetine overdose.

Consider contacting a Poison Center (1-800-221-2222) or a medical toxicologist for additional overdosage management recommendations.

11 DESCRIPTION

Fluoxetine hydrochloride is a selective serotonin reuptake inhibitor for oral administration. It is designated (±)-N-methyl-3-phenyl-3-[(α,α,α-trifluoro-p-tolyl)oxy]propylamine hydrochloride and has the empirical formula of C17H18F3NO•HCl. Its molecular weight is 345.79. The structural formula is:

Fluoxetine hydrochloride is a white to off-white crystalline solid with a solubility of 14 mg/mL in water.

Each scored tablet contains fluoxetine hydrochloride equivalent to 60 mg (194 μmol) of fluoxetine. In addition, each scored tablet also contains the following inactive ingredients: mannitol, microcrystalline cellulose, maize starch, povidone, hypromellose, magnesium stearate, titanium dioxide, sucrose, glycerol, and polysorbate.

12 CLINICAL PHARMACOLOGY

12.1 Mechanism of Action

Although the exact mechanism of fluoxetine is unknown, it is presumed to be linked to its inhibition of CNS neuronal uptake of serotonin.

12.2 Pharmacodynamics

Studies at clinically relevant doses in man have demonstrated that fluoxetine blocks the uptake of serotonin into human platelets. Studies in animals also suggest that fluoxetine is a much more potent uptake inhibitor of serotonin than of norepinephrine. Antagonism of muscarinic, histaminergic, and α1-adrenergic receptors has been hypothesized to be associated with various anticholinergic, sedative, and cardiovascular effects of classical TCA drugs. Fluoxetine binds to these and other membrane receptors from brain tissue much less potently in vitro than do the tricyclic drugs.

12.3 Pharmacokinetics

Systemic bioavailability—In man, following a single, oral dose of fluoxetine 60 mg tablet, USP, the peak plasma concentration of fluoxetine and time to achieve peak plasma concentration were 49.6 ± 10.0 ng/mL, and 7.20 ± 1.41 hours, respectively (both values are mean ± SD).

The capsule, tablet, and oral solution dosage forms of fluoxetine are bioequivalent. The exposure (Cmax, AUC) to fluoxetine was similar after administration of either 1 × 60 mg fluoxetine tablet USP or 3 × 20 mg fluoxetine tablets. Food does not appear to affect the systemic bioavailability of fluoxetine, although it may delay its absorption by 1 to 2 hours, which is probably not clinically significant. Thus, fluoxetine may be administered with or without food.

Protein binding—Over the concentration range from 200 to 1000 ng/mL, approximately 94.5% of fluoxetine is bound in vitro to human serum proteins, including albumin and α1-glycoprotein. The interaction between fluoxetine and other highly protein-bound drugs has not been fully evaluated, but may be important.

Enantiomers—Fluoxetine is a racemic mixture (50/50) of R-fluoxetine and S-fluoxetine enantiomers. In animal models, both enantiomers are specific and potent serotonin uptake inhibitors with essentially equivalent pharmacologic activity. The S-fluoxetine enantiomer is eliminated more slowly and is the predominant enantiomer present in plasma at steady state.

Metabolism—Fluoxetine is extensively metabolized in the liver to norfluoxetine and a number of other unidentified metabolites. The only identified active metabolite, norfluoxetine, is formed by demethylation of fluoxetine. In animal models, S-norfluoxetine is a potent and selective inhibitor of serotonin uptake and has activity essentially equivalent to R- or S-fluoxetine. R-norfluoxetine is significantly less potent than the parent drug in the inhibition of serotonin uptake. The primary route of elimination appears to be hepatic metabolism to inactive metabolites excreted by the kidney.

Variability in metabolism—A subset (about 7%) of the population has reduced activity of the drug metabolizing enzyme cytochrome P450 2D6 (CYP2D6). Such individuals are referred to as “poor metabolizers” of drugs such as debrisoquin, dextromethorphan, and the TCAs. In a study involving labeled and unlabeled enantiomers administered as a racemate, these individuals metabolized S-fluoxetine at a slower rate and thus achieved higher concentrations of S-fluoxetine. Consequently, concentrations of S-norfluoxetine at steady state were lower. The metabolism of R-fluoxetine in these poor metabolizers appears normal. When compared with normal metabolizers, the total sum at steady state of the plasma concentrations of the 4 active enantiomers was not significantly greater among poor metabolizers. Thus, the net pharmacodynamic activities were essentially the same. Alternative, nonsaturable pathways (non-2D6) also contribute to the metabolism of fluoxetine. This explains how fluoxetine achieves a steady-state concentration rather than increasing without limit.

Because fluoxetine’s metabolism, like that of a number of other compounds including TCAs and other SSRIs, involves the CYP2D6 system, concomitant therapy with drugs also metabolized by this enzyme system (such as the TCAs) may lead to drug interactions [see Drug Interactions (7.6)].

Accumulation and slow elimination—The relatively slow elimination of fluoxetine (elimination half-life of 1 to 3 days after acute administration and 4 to 6 days after chronic administration) and its active metabolite, norfluoxetine (elimination half-life of 4 to 16 days after acute and chronic administration), leads to significant accumulation of these active species in chronic use and delayed attainment of steady state, even when a fixed dose is used [see Warnings and Precautions (5.14)]. After 30 days of dosing at 40 mg/day, plasma concentrations of fluoxetine in the range of 91 to 302 ng/mL and norfluoxetine in the range of 72 to 258 ng/mL have been observed. Plasma concentrations of fluoxetine were higher than those predicted by single-dose studies, because fluoxetine’s metabolism is not proportional to dose. Norfluoxetine, however, appears to have linear pharmacokinetics. Its mean terminal half-life after a single dose was 8.6 days and after multiple dosing was 9.3 days. Steady-state levels after prolonged dosing are similar to levels seen at 4 to 5 weeks.

The long elimination half-lives of fluoxetine and norfluoxetine assure that, even when dosing is stopped, active drug substance will persist in the body for weeks (primarily depending on individual patient characteristics, previous dosing regimen, and length of previous therapy at discontinuation). This is of potential consequence when drug discontinuation is required or when drugs are prescribed that might interact with fluoxetine and norfluoxetine following the discontinuation of fluoxetine.

Liver disease—As might be predicted from its primary site of metabolism, liver impairment can affect the elimination of fluoxetine. The elimination half-life of fluoxetine was prolonged in a study of cirrhotic patients, with a mean of 7.6 days compared with the range of 2 to 3 days seen in subjects without liver disease; norfluoxetine elimination was also delayed, with a mean duration of 12 days for cirrhotic patients compared with the range of 7 to 9 days in normal subjects. This suggests that the use of fluoxetine in patients with liver disease must be approached with caution. If fluoxetine is administered to patients with liver disease, a lower or less frequent dose should be used [see Dosage and Administration (2.5) and Use in Specific Populations (8.6)].

Renal disease—In depressed patients on dialysis (N = 12), fluoxetine administered as 20 mg once daily for 2 months produced steady-state fluoxetine and norfluoxetine plasma concentrations comparable with those seen in patients with normal renal function. While the possibility exists that renally excreted metabolites of fluoxetine may accumulate to higher levels in patients with severe renal dysfunction, use of a lower or less frequent dose is not routinely necessary in renally impaired patients.

Geriatric pharmacokinetics—The disposition of single doses of fluoxetine in healthy elderly subjects (> 65 years of age) did not differ significantly from that in younger normal subjects. However, given the long half-life and nonlinear disposition of the drug, a single-dose study is not adequate to rule out the possibility of altered pharmacokinetics in the elderly, particularly if they have systemic illness or are receiving multiple drugs for concomitant diseases. The effects of age upon the metabolism of fluoxetine have been investigated in 260 elderly but otherwise healthy depressed patients (≥ 60 years of age) who received 20 mg fluoxetine for 6 weeks. Combined fluoxetine plus norfluoxetine plasma concentrations were 209.3 ± 85.7 ng/mL at the end of 6 weeks. No unusual age-associated pattern of adverse reactions was observed in those elderly patients.

Pediatric pharmacokinetics (children and adolescents)—Fluoxetine pharmacokinetics were evaluated in 21 pediatric patients (10 children ages 6 to < 13, 11 adolescents ages 13 to < 18) diagnosed with MDD or OCD. Fluoxetine 20 mg/day was administered for up to 62 days. The average steady-state concentrations of fluoxetine in these children were 2-fold higher than in adolescents (171 and 86 ng/mL, respectively). The average norfluoxetine steady-state concentrations in these children were 1.5-fold higher than in adolescents (195 and 113 ng/mL, respectively). These differences can be almost entirely explained by differences in weight. No gender-associated difference in fluoxetine pharmacokinetics was observed. Similar ranges of fluoxetine and norfluoxetine plasma concentrations were observed in another study in 94 pediatric patients (ages 8 to < 18) diagnosed with MDD.

Higher average steady-state fluoxetine and norfluoxetine concentrations were observed in children relative to adults; however, these concentrations were within the range of concentrations observed in the adult population. As in adults, fluoxetine and norfluoxetine accumulated extensively following multiple oral dosing; steady-state concentrations were achieved within 3 to 4 weeks of daily dosing.

13 NONCLINICAL TOXICOLOGY

13.1 Carcinogenesis, Mutagenesis, and Impairment of Fertility

Carcinogenesis—The dietary administration of fluoxetine to rats and mice for 2 years at doses of up to 10 and 12 mg/kg/day, respectively (approximately 1.2 and 0.7 times, respectively, the MRHD of 80 mg on a mg/m^2 basis), produced no evidence of carcinogenicity.

Mutagenesis—Fluoxetine and norfluoxetine have been shown to have no genotoxic effects based on the following assays: bacterial mutation assay, DNA repair assay in cultured rat hepatocytes, mouse lymphoma assay, and in vivo sister chromatid exchange assay in Chinese hamster bone marrow cells.

Impairment of fertility—Two fertility studies conducted in adult rats at doses of up to 7.5 and 12.5 mg/kg/day (approximately 0.9 and 1.5 times the MRHD on a mg/m^2 basis) indicated that fluoxetine had no adverse effects on fertility. However, adverse effects on fertility were seen when juvenile rats were treated with fluoxetine [see Use in Specific Populations (8.4)].

13.2 Animal Toxicology and/or Pharmacology

Phospholipids are increased in some tissues of mice, rats, and dogs given fluoxetine chronically. This effect is reversible after cessation of fluoxetine treatment. Phospholipid accumulation in animals has been observed with many cationic amphiphilic drugs, including fenfluramine, imipramine, and ranitidine. The significance of this effect in humans is unknown.

14 CLINICAL STUDIES

Efficacy for fluoxetine was established for the:

- Acute and maintenance treatment of MDD in adults, and children and adolescents (8 to 18 years) in 7 short-term and 2 long-term, placebo-controlled trials [see Clinical Studies (14.1)].
- Acute treatment of obsessions and compulsions in adults, and children and adolescents (7 to 17 years) with OCD in 3 short-term, placebo-controlled trials [see Clinical Studies (14.2)].
- Acute and maintenance treatment of binge-eating and vomiting behaviors in adult patients with moderate to severe Bulimia Nervosa in 3 short-term and 1 long-term, placebo-controlled trials [see Clinical Studies (14.3)].
- Acute treatment of Panic Disorder, with or without agoraphobia, in adult patients in 2 short-term, placebo-controlled trials [see Clinical Studies (14.4)].

14.1 Major Depressive Disorder

Daily Dosing

Adult—The efficacy of fluoxetine was studied in 5- and 6-week placebo-controlled trials with depressed adult and geriatric outpatients (≥ 18 years of age) whose diagnoses corresponded most closely to the DSM-III (currently DSM-IV) category of MDD. Fluoxetine was shown to be significantly more effective than placebo as measured by the Hamilton Depression Rating Scale (HAM-D). Fluoxetine was also significantly more effective than placebo on the HAM-D subscores for depressed mood, sleep disturbance, and the anxiety subfactor.

Two 6-week controlled studies (N = 671, randomized) comparing fluoxetine 20 mg and placebo have shown fluoxetine 20 mg daily to be effective in the treatment of elderly patients (≥ 60 years of age) with MDD. In these studies, fluoxetine produced a significantly higher rate of response and remission as defined, respectively, by a 50% decrease in the HAM-D score and a total endpoint HAM-D score of ≤ 8. Fluoxetine was well tolerated and the rate of treatment discontinuations due to adverse reactions did not differ between fluoxetine (12%) and placebo (9%).

A study was conducted involving depressed outpatients who had responded (modified HAMD-17 score of ≤ 7 during each of the last 3 weeks of open-label treatment and absence of MDD by DSM-III-R criteria) by the end of an initial 12-week, open-treatment phase on fluoxetine 20 mg/day. These patients (N = 298) were randomized to continuation on double-blind fluoxetine 20 mg/day or placebo. At 38 weeks (50 weeks total), a statistically significantly lower relapse rate (defined as symptoms sufficient to meet a diagnosis of MDD for 2 weeks or a modified HAMD-17 score of ≥ 14 for 3 weeks) was observed for patients taking fluoxetine compared with those on placebo.

Pediatric (children and adolescents)—The efficacy of fluoxetine 20 mg/day in children and adolescents (N = 315 randomized; 170 children ages 8 to < 13, 145 adolescents ages 13 to ≤ 18) was studied in two 8- to 9-week placebo-controlled clinical trials in depressed outpatients whose diagnoses corresponded most closely to the DSM-III-R or DSM-IV category of MDD. In both studies independently, fluoxetine produced a statistically significantly greater mean change on the Childhood Depression Rating Scale-Revised (CDRS-R) total score from baseline to endpoint than did placebo.

Subgroup analyses on the CDRS-R total score did not suggest any differential responsiveness on the basis of age or gender.

14.2 Obsessive Compulsive Disorder

Adult—The effectiveness of fluoxetine for the treatment of OCD was demonstrated in two 13-week, multicenter, parallel-group studies (studies 1 and 2) of adult outpatients who received fixed fluoxetine doses of 20, 40, or 60 mg/day (on a once-a-day schedule, in the morning) or placebo. Patients in both studies had moderate to severe OCD (DSM-III-R), with mean baseline ratings on the Yale-Brown Obsessive Compulsive Scale (YBOCS, total score) ranging from 22 to 26. In study 1, patients receiving fluoxetine experienced mean reductions of approximately 4 to 6 units on the YBOCS total score, compared with a 1-unit reduction for placebo patients. In study 2, patients receiving fluoxetine experienced mean reductions of approximately 4 to 9 units on the YBOCS total score, compared with a 1-unit reduction for placebo patients. While there was no indication of a dose-response relationship for effectiveness in study 1, a dose-response relationship was observed in study 2, with numerically better responses in the 2 higher dose groups. Table 5 provides the outcome classification by treatment group on the Clinical Global Impression (CGI) improvement scale for studies 1 and 2 combined:

Table 5. Outcome Classification (%) on CGI Improvement Scale for Completers in Pool of Two OCD Studies
 |  | Fluoxetine
Outcome Classification | Placebo | 20 mg | 40 mg | 60 mg
Worse | 8% | 0% | 0% | 0%
No change | 64% | 41% | 33% | 29%
Minimally improved | 17% | 23% | 28% | 24%
Much improved | 8% | 28% | 27% | 28%
Very much improved | 3% | 8% | 12% | 19%

Exploratory analyses for age and gender effects on outcome did not suggest any differential responsiveness on the basis of age or sex.

Pediatric (children and adolescents)—In one 13-week clinical trial in pediatric patients (N = 103 randomized; 75 children ages 7 to < 13, 28 adolescents ages 13 to < 18) with OCD (DSM-IV), patients received fluoxetine 10 mg/day for 2 weeks, followed by 20 mg/day for 2 weeks. The dose was then adjusted in the range of 20 to 60 mg/day on the basis of clinical response and tolerability. Fluoxetine produced a statistically significantly greater mean change from baseline to endpoint than did placebo as measured by the Children’s Yale-Brown Obsessive Compulsive Scale (CY-BOCS).

Subgroup analyses on outcome did not suggest any differential responsiveness on the basis of age or gender.

14.3 Bulimia Nervosa

The effectiveness of fluoxetine for the treatment of bulimia was demonstrated in two 8-week and one 16-week, multicenter, parallel-group studies of adult outpatients meeting DSM-III-R criteria for bulimia. Patients in the 8-week studies received either 20 or 60 mg/day of fluoxetine or placebo in the morning. Patients in the 16-week study received a fixed fluoxetine dose of 60 mg/day (once a day) or placebo. Patients in these 3 studies had moderate to severe bulimia with median binge-eating and vomiting frequencies ranging from 7 to 10 per week and 5 to 9 per week, respectively. In these 3 studies, fluoxetine 60 mg, but not 20 mg, was statistically significantly superior to placebo in reducing the number of binge-eating and vomiting episodes per week. The statistically significantly superior effect of 60 mg versus placebo was present as early as week 1 and persisted throughout each study.

The fluoxetine-related reduction in bulimic episodes appeared to be independent of baseline depression as assessed by the HAM-D. In each of these 3 studies, the treatment effect, as measured by differences between fluoxetine 60 mg and placebo on median reduction from baseline in frequency of bulimic behaviors at endpoint, ranged from 1 to 2 episodes per week for binge-eating and 2 to 4 episodes per week for vomiting. The size of the effect was related to baseline frequency, with greater reductions seen in patients with higher baseline frequencies. Although some patients achieved freedom from binge-eating and purging as a result of treatment, for the majority, the benefit was a partial reduction in the frequency of binge-eating and purging.

In a longer-term trial, 150 patients meeting DSM-IV criteria for Bulimia Nervosa, purging subtype, who had responded during a single-blind, 8-week, acute-treatment phase with fluoxetine 60 mg/day, were randomized to continuation of fluoxetine 60 mg/day or placebo, for up to 52 weeks of observation for relapse. Response during the single-blind phase was defined by having achieved at least a 50% decrease in vomiting frequency compared with baseline. Relapse during the double-blind phase was defined as a persistent return to baseline vomiting frequency or physician judgment that the patient had relapsed. Patients receiving continued fluoxetine 60 mg/day experienced a significantly longer time to relapse over the subsequent 52 weeks compared with those receiving placebo.

14.4 Panic Disorder

The effectiveness of fluoxetine in the treatment of Panic Disorder was demonstrated in 2 double-blind, randomized, placebo-controlled, multicenter studies of adult outpatients who had a primary diagnosis of Panic Disorder (DSM-IV), with or without agoraphobia.

Study 1 (N = 180 randomized) was a 12-week, flexible-dose study. Fluoxetine was initiated at 10 mg/day for the first week, after which patients were dosed in the range of 20 to 60 mg/day on the basis of clinical response and tolerability. A statistically significantly greater percentage of fluoxetine-treated patients were free from panic attacks at endpoint than placebo-treated patients, 42% versus 28%, respectively.

Study 2 (N = 214 randomized) was a 12-week, flexible-dose study. Fluoxetine was initiated at 10 mg/day for the first week, after which patients were dosed in a range of 20 to 60 mg/day on the basis of clinical response and tolerability. A statistically significantly greater percentage of fluoxetine-treated patients were free from panic attacks at endpoint than placebo-treated patients, 62% versus 44%, respectively.

16 HOW SUPPLIED/STORAGE AND HANDLING

16.1 How Supplied

Fluoxetine tablets, USP 60 mg, are available as 60-mg (fluoxetine base equivalent), film-coated, functional-scored, capsule-shaped, white tablets debossed with “FL 60” on one side (“FL” above the score and “60” below the score).

NDC 52427-576-30 | Bottle of 30 tablets

16.2 Storage and Handling

Store at 20°C to 25°C (68°F to 77°F) [See USP Controlled Room Temperature]. Protect from light.

17 PATIENT COUNSELING INFORMATION

Advise the patient to read the FDA-approved patient labeling (Medication Guide).

Information on Medication Guide and Benefits/Risks of Fluoxetine

Healthcare providers should instruct their patients to read the Medication Guide before starting therapy with fluoxetine tablets and to reread it each time the prescription is renewed.

Healthcare providers should inform patients, their families, and their caregivers about the benefits and risks associated with treatment with fluoxetine tablets and should counsel them in its appropriate use. Healthcare providers should instruct patients, their families, and their caregivers to read the Medication Guide and should assist them in understanding its contents. Patients should be given the opportunity to discuss the contents of the Medication Guide and to obtain answers to any questions they may have.

Patients should be advised of the following issues and asked to alert their healthcare provider if these occur while taking fluoxetine tablets.

Suicidal Thoughts and Behaviors in Children, Adolescents, and Young Adults

Patients, their families, and their caregivers should be encouraged to be alert to the emergence of anxiety, agitation, panic attacks, insomnia, irritability, hostility, aggressiveness, impulsivity, akathisia (psychomotor restlessness), hypomania, mania, other unusual changes in behavior, worsening of depression, and suicidal ideation, especially early during antidepressant treatment and when the dose is adjusted up or down. Families and caregivers of patients should be advised to look for the emergence of such symptoms on a day-to-day basis, since changes may be abrupt. Such symptoms should be reported to the patient’s prescriber or health professional, especially if they are severe, abrupt in onset, or were not part of the patient’s presenting symptoms. Symptoms such as these may be associated with an increased risk for suicidal thinking and behavior and indicate a need for very close monitoring and possibly changes in the medication [see Boxed Warning and Warnings and Precautions (5.1)].

Serotonin Syndrome

Patients should be cautioned about the risk of serotonin syndrome with the concomitant use of fluoxetine and other serotonergic agents including triptans, tricyclic antidepressants, opioids, lithium, buspirone, tryptophan, amphetamines, and St. John’s Wort, and with drugs that impair metabolism of serotonin (in particular, MAOIs, both those intended to treat psychiatric disorders and also others, such as linezolid). Instruct patients to contact their healthcare provider or report to the emergency room if they experience signs or symptoms of serotonin syndrome [see Contraindications (4.1), Warnings and Precautions (5.2), and Drug Interactions (7.3)].

Allergic Reactions and Rash

Patients should be advised to notify their physician if they develop a rash or hives [see Warnings and Precautions (5.3)]. Patients should also be advised of the signs and symptoms associated with a severe allergic reaction, including swelling of the face, eyes, or mouth, or have trouble breathing. Patients should be cautioned to seek medical care immediately if they experience these symptoms.

Increased Risk of Bleeding

Inform patients about the concomitant use of fluoxetine and NSAIDs, aspirin, warfarin, or other drugs that affect coagulation since combined use of psychotropic drugs that interfere with serotonin reuptake and these agents have been associated with an increased risk of bleeding [see Warnings and Precautions (5.7) and Drug Interactions (7.4)]. Advise patients to call their doctor if they experience any increased or unusual bruising or bleeding while taking fluoxetine.

Angle-closure Glaucoma

Patients should be advised that taking fluoxetine can cause mild pupillary dilation, which in susceptible individuals, can lead to an episode of angle-closure glaucoma. Pre-existing glaucoma is almost always open-angle glaucoma because angle-closure glaucoma, when diagnosed, can be treated definitively with iridectomy. Open-angle glaucoma is not a risk factor for angle-closure glaucoma. Patients may wish to be examined to determine whether they are susceptible to angle closure, and have a prophylactic procedure (e.g., iridectomy), if they are susceptible [see Warnings and Precautions (5.8)].

Hyponatremia

Patients should be advised that hyponatremia has been reported as a result of treatment with SNRIs and SSRIs, including fluoxetine. Signs and symptoms of hyponatremia include headache, difficulty concentrating, memory impairment, confusion, weakness, and unsteadiness, which may lead to falls. More severe and/or acute cases have been associated with hallucination, syncope, seizure, coma, respiratory arrest, and death [see Warnings and Precautions (5.9)].

QT Prolongation

Patients should be advised that QT interval prolongation and ventricular arrhythmia including Torsades de Pointes have been reported in patients treated with fluoxetine. Signs and symptoms of ventricular arrhythmia include fast, slow, or irregular heart rate, dyspnea, syncope, or dizziness, which may indicate serious cardiac arrhythmia [see Warnings and Precautions (5.11)].

Potential for Cognitive and Motor Impairment

Fluoxetine may impair judgment, thinking, or motor skills. Patients should be advised to avoid driving a car or operating hazardous machinery until they are reasonably certain that their performance is not affected [see Warnings and Precautions (5.13)].

Use of Concomitant Medications

Patients should be advised to inform their physician if they are taking, or plan to take, any prescription medication, including Prozac® (fluoxetine hydrochloride), Symbyax® (olanzapine and fluoxetine hydrochloride capsules), Sarafem® (fluoxetine tablets), or over-the-counter drugs, including herbal supplements or alcohol. Patients should also be advised to inform their physicians if they plan to discontinue any medications they are taking while on fluoxetine.

Discontinuation of Treatment

Patients should be advised to take fluoxetine exactly as prescribed, and to continue taking fluoxetine as prescribed even after their symptoms improve. Patients should be advised that they should not alter their dosing regimen, or stop taking fluoxetine without consulting their physician [see Warnings and Precautions (5.15)]. Patients should be advised to consult with their healthcare provider if their symptoms do not improve with fluoxetine.

Sexual Dysfunction

Advise patients that use of fluoxetine may cause symptoms of sexual dysfunction in both male and female patients. Inform patients that they should discuss any changes in sexual function and potential management strategies with their healthcare provider [see Warnings and Precautions (5.16)].

Use in Specific Populations

Pregnancy—Advise pregnant women to notify their healthcare provider if they become pregnant or intend to become pregnant during treatment with Fluoxetine Tablets.

Advise patients that Fluoxetine Tablet use later in pregnancy may lead to increased risk for neonatal complications requiring prolonged hospitalization, respiratory support, tube feeding, and/or persistent pulmonary hypertension of the newborn (PPHN) [see Use in Specific Populations (8.1)].

Advise women that there is a pregnancy exposure registry that monitors pregnancy outcomes in women exposed to fluoxetine during pregnancy [see Use in Specific Populations (8.1)].

Lactation— Advise breastfeeding women using Fluoxetine Tablets to monitor infants for agitation, irritability, poor feeding and poor weight gain and to seek medical care if they notice these signs [see Use in Specific Populations (8.2)].

Pediatric use—Fluoxetine is approved for use in pediatric patients with MDD and OCD [see Boxed Warning and Warnings and Precautions (5.1)]. Limited evidence is available concerning the longer-term effects of fluoxetine on the development and maturation of children and adolescent patients. Height and weight should be monitored periodically in pediatric patients receiving fluoxetine [see Warnings and Precautions (5.6) and Use in Specific Populations (8.4)].

Symbyax and Prozac are registered trademarks of Eli Lilly and Company.

Sarafem is a registered trademark of Warner Chilcott.

Manufactured by:
Orion Pharmaceuticals
FN-02200 Espoo, Finland

Distributed by:
Almatica Pharma, Inc.
Pine Brook, NJ 07058 USA

Product of Finland

PI576-XX R

MEDICATION GUIDE

FLUOXETINE TABLETS

Read the Medication Guide that comes with fluoxetine before you start taking it and each time you get a refill. There may be new information. This Medication Guide does not take the place of talking to your healthcare provider about your medical condition or treatment. Talk with your healthcare provider if there is something you do not understand or want to learn more about.

What is the most important information I should know about fluoxetine?

Fluoxetine and other antidepressant medicines may cause serious side effects, including:

1. Suicidal thoughts or actions:

- Fluoxetine and other antidepressant medicines may increase suicidal thoughts or actions in some children, teenagers, or young adults within the first few months of treatment or when the dose is changed.
- Depression or other serious mental illnesses are the most important causes of suicidal thoughts or actions.
- Watch for these changes and call your healthcare provider right away if you notice:
- New or sudden changes in mood, behavior, actions, thoughts, or feelings, especially if severe.
- Pay particular attention to such changes when fluoxetine is started or when the dose is changed.

Keep all follow-up visits with your healthcare provider and call between visits if you are worried about symptoms.

Call your healthcare provider right away if you have any of the following symptoms, or call 911 if an emergency, especially if they are new, worse, or worry you:

- attempts to commit suicide
- acting on dangerous impulses
- acting aggressive or violent
- thoughts about suicide or dying
- new or worse depression
- new or worse anxiety or panic attacks
- feeling agitated, restless, angry, or irritable
- trouble sleeping
- an increase in activity or talking more than what is normal for you
- other unusual changes in behavior or mood

Call your healthcare provider right away if you have any of the following symptoms, or call 911 if an emergency. Fluoxetine may be associated with these serious side effects:

2. Serotonin Syndrome. This condition can be life-threatening and may include:

- agitation, hallucinations, coma, or other changes in mental status
- coordination problems or muscle twitching (overactive reflexes)
- racing heartbeat, high or low blood pressure
- sweating or fever
- nausea, vomiting, or diarrhea
- muscle rigidity
- dizziness
- flushing
- tremor
- seizures

3. Severe allergic reactions:

- trouble breathing
- swelling of the face, tongue, eyes, or mouth
- rash, itchy welts (hives) or blisters, alone or with fever or joint pain

4. Abnormal bleeding: Fluoxetine and other antidepressant medicines may increase your risk of bleeding or bruising, especially if you take the blood thinner warfarin (Coumadin®, Jantoven®), a nonsteroidal anti-inflammatory drug (NSAIDs, like ibuprofen or naproxen), or aspirin.

5. Visual problems:

- eye pain
- changes in vision
- swelling or redness in or around the eye

Only some people are at risk for these problems. You may want to undergo an eye examination to see if you are at risk and receive preventative treatment if you are.

6. Seizures or convulsions

7. Manic episodes:

- greatly increased energy
- severe trouble sleeping
- racing thoughts
- reckless behavior
- unusually grand ideas
- excessive happiness or irritability
- talking more or faster than usual

8. Changes in appetite or weight. Children and adolescents should have height and weight monitored during treatment.

9. Low salt (sodium) levels in the blood. Elderly people may be at greater risk for this. Symptoms may include:

- headache
- weakness or feeling unsteady
- confusion, problems concentrating, or thinking or memory problems

10. Changes in the electrical activity of your heart (QT prolongation and ventricular arrhythmia including Torsades de Pointes). This condition can be life threatening. The symptoms may include:

- fast, slow, or irregular heartbeat
- shortness of breath
- dizziness or fainting

11. Sexual problems (dysfunction). Taking selective serotonin reuptake inhibitors (SSRIs), including fluoxetine, may cause sexual problems.

Symptoms in males may include:

- Delayed ejaculation or inability to have an ejaculation
- Decreased sex drive
- Problems getting or keeping an erection

Symptoms in females may include:

- Decreased sex drive
- Delayed orgasm or inability to have an orgasm

Talk to your healthcare provider if you develop any changes in your sexual function or if you have any questions or concerns about sexual problems during treatment with fluoxetine. There may be treatments your healthcare provider can suggest.

Do not stop fluoxetine without first talking to your healthcare provider. Stopping fluoxetine too quickly may cause serious symptoms including:

- anxiety, irritability, high or low mood, feeling restless, or changes in sleep habits
- headache, sweating, nausea, dizziness
- electric shock-like sensations, shaking, confusion

What is fluoxetine?

Fluoxetine is a prescription medicine used to treat depression. It is important to talk with your healthcare provider about the risks of treating depression and also the risks of not treating it. You should discuss all treatment choices with your healthcare provider.

Fluoxetine is used to treat:

- Major Depressive Disorder (MDD)
- Obsessive Compulsive Disorder (OCD)
- Bulimia Nervosa*
- Panic Disorder*
- Depressive episodes associated with Bipolar I Disorder, taken with olanzapine (Zyprexa)*
- Treatment Resistant Depression (depression that has not gotten better with at least 2 other treatments), taken with olanzapine (Zyprexa)*

*Not approved for use in children.

Talk to your healthcare provider if you do not think that your condition is getting better with fluoxetine treatment.

Who should not take fluoxetine?

Do not take fluoxetine if you:

- are allergic to fluoxetine hydrochloride or any of the ingredients in fluoxetine. See the end of this Medication Guide for a complete list of ingredients in fluoxetine.
- take a Monoamine Oxidase Inhibitor (MAOI). Ask your healthcare provider or pharmacist if you are not sure if you take an MAOI, including the antibiotic linezolid.
- Do not take an MAOI within 5 weeks of stopping fluoxetine unless directed to do so by your physician.
- Do not start fluoxetine if you stopped taking an MAOI in the last 2 weeks unless directed to do so by your physician.

People who take fluoxetine close in time to an MAOI may have serious or even life-threatening side effects. Get medical help right away if you have any of these symptoms:

- high fever
- uncontrolled muscle spasms
- stiff muscles
- rapid changes in heart rate or blood pressure
- confusion
- loss of consciousness (pass out)

- take Mellaril® (thioridazine). Do not take Mellaril® within 5 weeks of stopping fluoxetine because this can cause serious heart rhythm problems or sudden death.
- take the antipsychotic medicine pimozide (Orap®) because this can cause serious heart problems.

What should I tell my healthcare provider before taking fluoxetine? Ask if you are not sure.

Before starting fluoxetine, tell your healthcare provider if you:

- are taking certain drugs or treatments such as:
- Triptans used to treat migraine headache
- Medicines used to treat mood, anxiety, psychotic, or thought disorders, including tricyclics, lithium, SSRIs, SNRIs, MAOIs, or antipsychotics
- Tramadol, fentanyl, meperidine, methadone, or other opioids
- Amphetamines
- Over-the-counter supplements such as tryptophan or St. John’s Wort
- Electroconvulsive therapy (ECT)
- have liver problems
- have kidney problems
- have heart problems
- have or had seizures or convulsions
- have bipolar disorder or mania
- have low sodium levels in your blood
- have a history of a stroke
- have high blood pressure
- have or had bleeding problems
- are pregnant or plan to become pregnant. Taking Fluoxetine Tablets late in pregnancy may lead to an increased risk of certain problems in your newborn. Talk to your healthcare provider about the benefits and risks of treating depression during pregnancy.
  - If you become pregnant while taking Fluoxetine Tablets, talk to your healthcare provider about registering with the National Pregnancy Registry for Antidepressants. You can register by calling 1-866-961-2388 or go to https://womensmentalhealth.org/research/pregnancyregistry/antidepressants/.
- are breast-feeding or plan to breast-feed. Fluoxetine may pass into your breast milk. Talk to your healthcare provider about the best way to feed your baby if taking Fluoxetine Tablets.

Tell your healthcare provider about all the medicines that you take, including prescription and nonprescription medicines, vitamins, and herbal supplements. Fluoxetine and some medicines may interact with each other, may not work as well, or may cause serious side effects.

Your healthcare provider or pharmacist can tell you if it is safe to take fluoxetine with your other medicines. Do not start or stop any medicine while taking fluoxetine without talking to your healthcare provider first.

If you take fluoxetine, you should not take any other medicines that contain fluoxetine hydrochloride including:

- Symbyax® (olanzapine and fluoxetine hydrochloride)
- Sarafem® (fluoxetine)
- Prozac®
- Prozac® Weekly™

How should I take fluoxetine?

- Take fluoxetine exactly as prescribed. Your healthcare provider may need to change the dose of fluoxetine until it is the right dose for you. Each tablet can be broken in half (along the functional score).
- Fluoxetine may be taken with or without food.
- If you miss a dose of fluoxetine, take the missed dose as soon as you remember. If it is almost time for the next dose, skip the missed dose and take your next dose at the regular time. Do not take two doses of fluoxetine at the same time.
- If you take too much fluoxetine, call your healthcare provider or poison control center right away, or get emergency treatment.

What should I avoid while taking fluoxetine?

Fluoxetine can cause sleepiness or may affect your ability to make decisions, think clearly, or react quickly. You should not drive, operate heavy machinery, or do other dangerous activities until you know how fluoxetine affects you. Do not drink alcohol while using fluoxetine.

What are the possible side effects of fluoxetine?

Fluoxetine may cause serious side effects, including:

- See “What is the most important information I should know about fluoxetine?”
- Problems with blood sugar control. People who have diabetes and take fluoxetine may have problems with low blood sugar while taking fluoxetine. High blood sugar can happen when fluoxetine is stopped. Your healthcare provider may need to change the dose of your diabetes medicines when you start or stop taking fluoxetine.
- Feeling anxious or trouble sleeping

Common possible side effects in people who take fluoxetine include:

- unusual dreams
- sexual problems
- loss of appetite, diarrhea, indigestion, nausea or vomiting, weakness, or dry mouth
- flu symptoms
- feeling tired or fatigued
- change in sleep habits
- yawning
- sinus infection or sore throat
- tremor or shaking
- sweating
- feeling anxious or nervous
- hot flashes
- rash

Other side effects in children and adolescents include:

- increased thirst
- abnormal increase in muscle movement or agitation
- nose bleed
- urinating more often
- heavy menstrual periods
- possible slowed growth rate and weight change. Your child’s height and weight should be monitored during treatment with fluoxetine.

Tell your healthcare provider if you have any side effect that bothers you or that does not go away. These are not all the possible side effects of fluoxetine. For more information, ask your healthcare provider or pharmacist.

CALL YOUR DOCTOR FOR MEDICAL ADVICE ABOUT SIDE EFFECTS. YOU MAY REPORT SIDE EFFECTS TO THE FDA AT 1-800-FDA-1088.

How should I store fluoxetine?

- Store fluoxetine at room temperature between 68°F and 77°F (20°C to 25°C).
- Keep fluoxetine away from light.
- Keep fluoxetine bottle closed tightly.

Keep fluoxetine and all medicines out of the reach of children.

General information about fluoxetine

Medicines are sometimes prescribed for purposes other than those listed in a Medication Guide. Do not use fluoxetine for a condition for which it was not prescribed. Do not give fluoxetine to other people, even if they have the same condition. It may harm them.

This Medication Guide summarizes the most important information about fluoxetine. If you would like more information, talk with your healthcare provider. You may ask your healthcare provider or pharmacist for information about fluoxetine that is written for healthcare professionals.

For more information about fluoxetine call 1-877-447-7979.

What are the ingredients in fluoxetine tablets, 60 mg?

Active ingredient: fluoxetine hydrochloride

Inactive ingredients: mannitol, microcrystalline cellulose, maize starch, povidone, hypromellose, magnesium stearate, titanium dioxide, sucrose, glycerol, and polysorbate.

This Medication Guide has been approved by the US Food and Drug Administration.

Symbyax and Prozac are registered trademarks of Eli Lilly and Company.
Prozac Weekly is a registered trademark of Eli Lilly and Company.
Sarafem is a registered trademark of Warner Chilcott.
Mellaril is a registered trademark of Novartis AG Corporation.
Orap is a registered trademark of Teva Pharmaceuticals USA.
Coumadin is a registered trademark of Bristol Myers Squibb.
Jantoven is a registered trademark of Upsher-Smith Laboratories Inc.

Manufactured by:
Orion Pharmaceuticals
FN-02200
Espoo, Finland

Distributed by:
Almatica Pharma, Inc.
Pine Brook, NJ 07058 USA

Product of Finland

Revised: 8/2023
PL576-XX R

PRINCIPAL DISPLAY PANEL - BOTTLE

NDC 52427-576-30

Fluoxetine Tablets, USP
60 mg*

PHARMACIST: Dispense the accompanying Medication Guide to each patient

Rx only
30 TABLETS

*Each tablet contains fluoxetine hydrochloride, USP, equivalent to 60 mg fluoxetine.